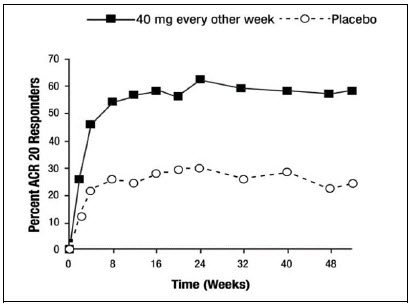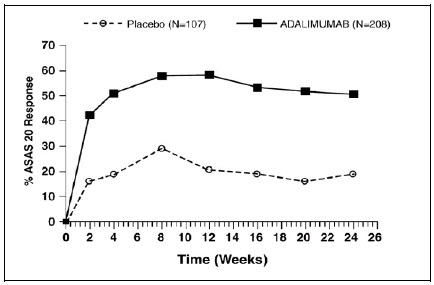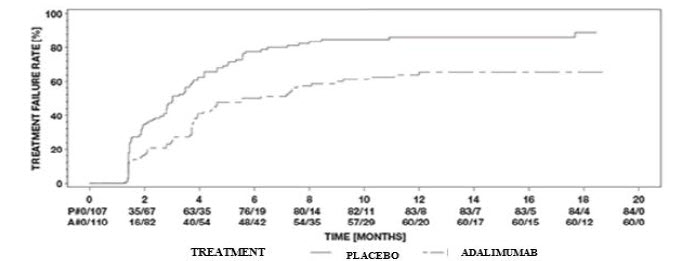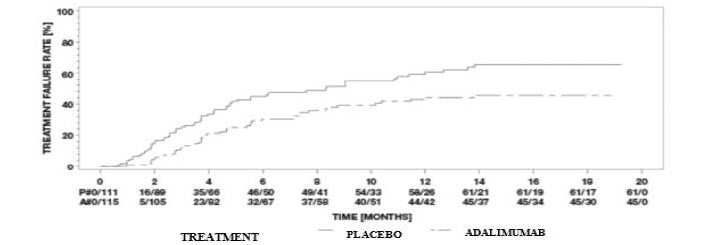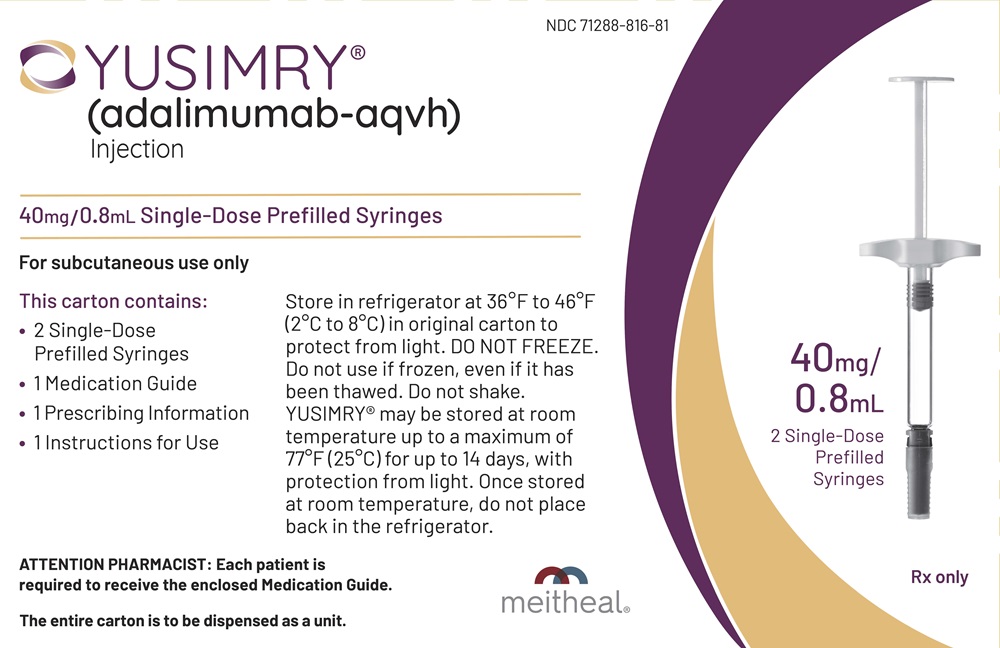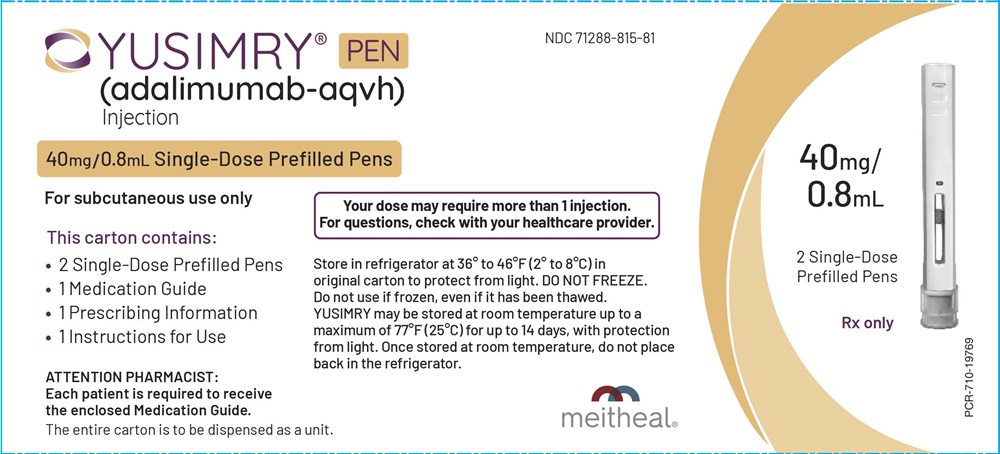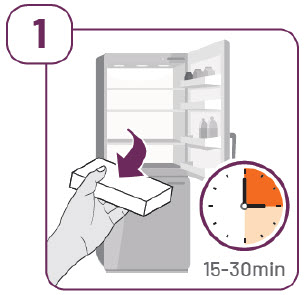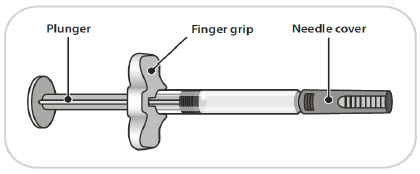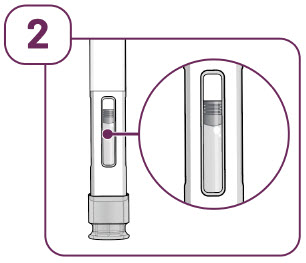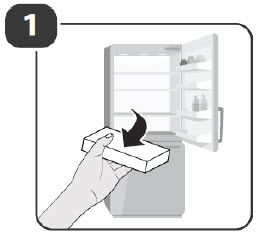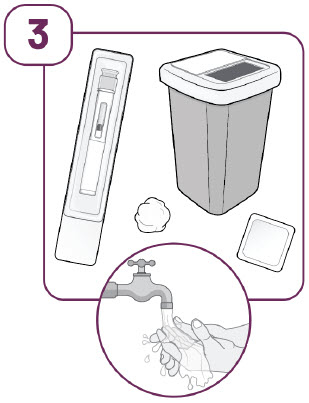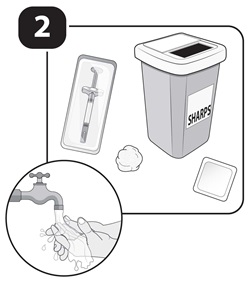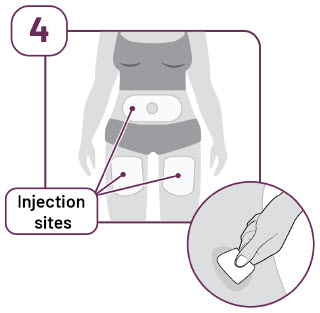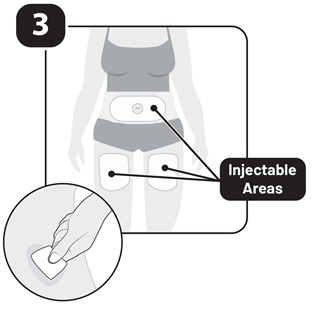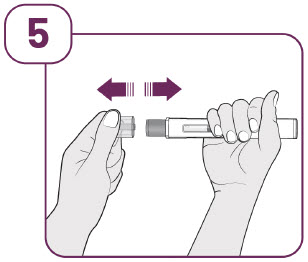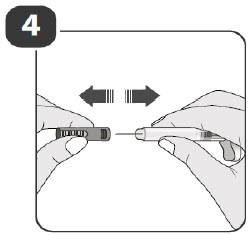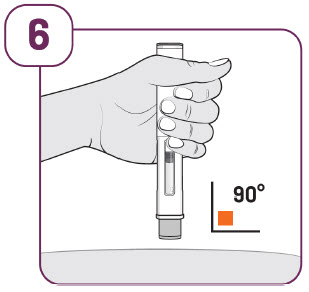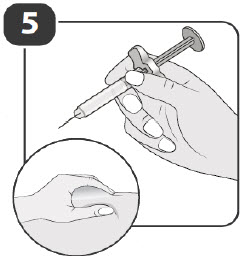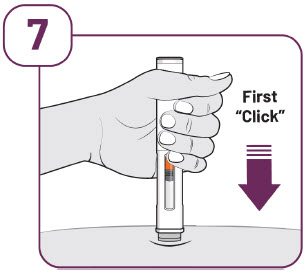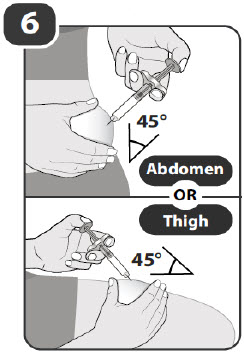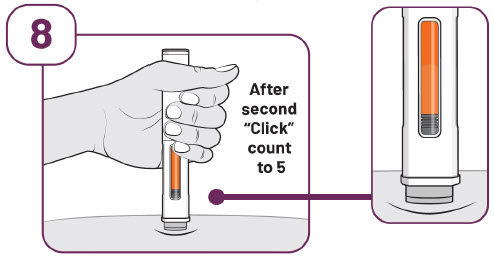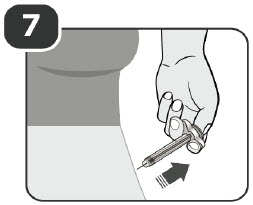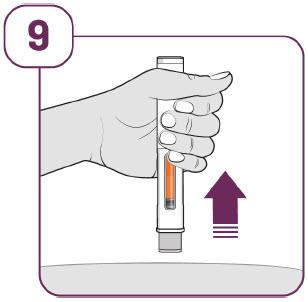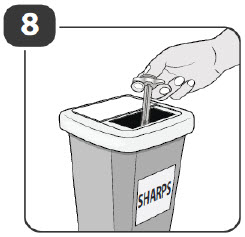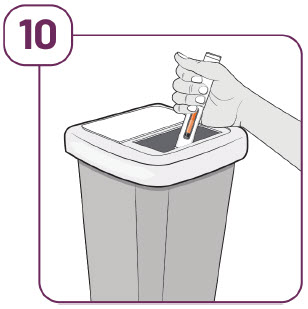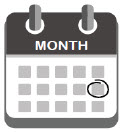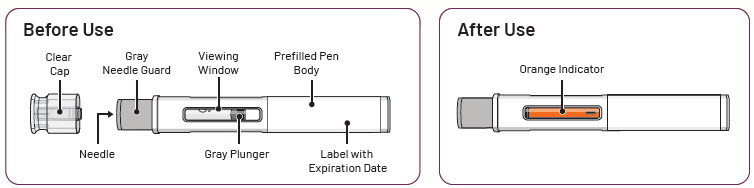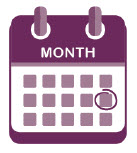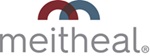 DRUG LABEL: YUSIMRY
NDC: 71288-816 | Form: INJECTION, SOLUTION
Manufacturer: Meitheal Pharmaceuticals Inc.
Category: prescription | Type: HUMAN PRESCRIPTION DRUG LABEL
Date: 20251031

ACTIVE INGREDIENTS: ADALIMUMAB 40 mg/0.8 mL
INACTIVE INGREDIENTS: HISTIDINE; HISTIDINE MONOHYDROCHLORIDE MONOHYDRATE; GLYCINE; SODIUM CHLORIDE; POLYSORBATE 80; WATER

HIGHLIGHTS OF PRESCRIBING INFORMATION

These highlights do not include all the information needed to use YUSIMRY safely and effectively. See full prescribing information for YUSIMRY.
YUSIMRY (adalimumab-aqvh) injection, for subcutaneous use
Initial U.S. Approval: 2021
YUSIMRY (adalimumab-aqvh) is biosimilar [Biosimilar means that the biological product is approved based on data demonstrating that it is highly similar to an FDA-approved biological product, known as a reference product, and that there are no clinically meaningful differences between the biosimilar product and the reference product. Biosimilarity of YUSIMRY has been demonstrated for the condition(s) of use (e.g., indication(s), dosing regimen(s)), strength(s), dosage form(s), and route(s) of administration described in its Full Prescribing Information.] to HUMIRA (adalimumab)

WARNING: SERIOUS INFECTIONS and MALIGNANCY

See full prescribing information for complete boxed warning.

SERIOUS INFECTIONS (5.1, 6.1):

- Increased risk of serious infections leading to hospitalization or death, including tuberculosis (TB), bacterial sepsis, invasive fungal infections (such as histoplasmosis), and infections due to other opportunistic pathogens.
- Discontinue YUSIMRY if a patient develops a serious infection or sepsis during treatment.
- Perform test for latent TB; if positive, start treatment for TB prior to starting YUSIMRY.
- Monitor all patients for active TB during treatment, even if initial latent TB test is negative.

MALIGNANCY (5.2):

- Lymphoma and other malignancies, some fatal, have been reported in children and adolescent patients treated with TNF blockers including adalimumab products.
- Post-marketing cases of hepatosplenic T-cell lymphoma (HSTCL), a rare type of T-cell lymphoma, have occurred in adolescent and young adults with inflammatory bowel disease treated with TNF blockers including adalimumab products.

RECENT MAJOR CHANGES

Warnings and Precautions, Autoimmunity (5.9) | 7/2025

1 INDICATIONS AND USAGE

YUSIMRY is a tumor necrosis factor (TNF) blocker indicated for:

- Reducing signs and symptoms, inducing major clinical response, inhibiting the progression of structural damage, and improving physical function in adult patients with moderately to severely active rheumatoid arthritis. (1.1)
- Reducing signs and symptoms of moderately to severely active polyarticular juvenile idiopathic arthritis in patients 2 years of age and older. (1.2)
- Reducing signs and symptoms, inhibiting the progression of structural damage, and improving physical function in adult patients with active psoriatic arthritis. (1.3)
- Reducing signs and symptoms in adult patients with active ankylosing spondylitis. (1.4)
- Treatment of moderately to severely active Crohn’s disease in adults and pediatric patients 6 years of age and older. (1.5)
- Treatment of moderately to severely active ulcerative colitis in adult patients. (1.6)
  Limitations of Use: Effectiveness has not been established in patients who have lost response to or were intolerant to TNF blockers.
- Treatment of adult patients with moderate to severe chronic plaque psoriasis who are candidates for systemic therapy or phototherapy, and when other systemic therapies are medically less appropriate. (1.7)
- Treatment of moderate to severe hidradenitis suppurativa in adult patients. (1.8)
- Treatment of non-infectious intermediate, posterior, and panuveitis in adults. (1.9)

2 DOSAGE AND ADMINISTRATION

- Administer by subcutaneous injection (2)

Rheumatoid Arthritis, Psoriatic Arthritis, Ankylosing Spondylitis (2.2):

- Adults: 40 mg every other week.

Some patients with RA not receiving methotrexate may benefit from increasing the dosage to 40 mg every week or 80 mg every other week.

Juvenile Idiopathic Arthritis (2.3):

Pediatric Weight 2 Years of Age and Older | Recommended Dosage
30 kg (66 lbs) and greater | 40 mg every other week

Crohn's Disease (2.4):

- Adults: 160 mg on Day 1 (given in one day or split over two consecutive days); 80 mg on Day 15; and 40 mg every other week starting on Day 29.
- Pediatric Patients 6 Years of Age and Older:

Pediatric Weight | Recommended Dosage
Pediatric Weight | Days 1 and 15 | Starting on Day 29
40 kg (88 lbs) and greater | Day 1: 160 mg (single dose or split over two consecutive days); Day 15: 80 mg | 40 mg every other week

Ulcerative Colitis (2.5):

- Adults: 160 mg on Day 1 (given in one day or split over two consecutive days), 80 mg on Day 15 and 40 mg every other week starting on Day 29. Discontinue in patients without evidence of clinical remission by eight weeks (Day 57).

Plaque Psoriasis or Adult Uveitis (2.6):

- Adults: 80 mg initial dose, followed by 40 mg every other week starting one week after initial dose.

Hidradenitis Suppurativa (2.7):

- Adults:
  - Day 1: 160 mg (given in one day or split over two consecutive days)
  - Day 15: 80 mg
  - Day 29 and subsequent doses: 40 mg every week or 80 mg every other week

3 DOSAGE FORMS AND STRENGTHS

Injection:

- Single-dose prefilled pen (YUSIMRY Pen): 40 mg/0.8mL (3)
- Single-dose prefilled glass syringe: 40 mg/0.8 mL (3)

4 CONTRAINDICATIONS

- None (4)

5 WARNINGS AND PRECAUTIONS

- Serious infections: Do not start YUSIMRY during an active infection. If an infection develops, monitor carefully, and stop YUSIMRY if infection becomes serious. (5.1)
- Invasive fungal infections: For patients who develop a systemic illness on YUSIMRY, consider empiric antifungal therapy for those who reside or travel to regions where mycoses are endemic. (5.1)
- Malignancies: Incidence of malignancies was greater in adalimumab-treated patients than in controls. (5.2)
- Anaphylaxis or serious hypersensitivity reactions may occur. (5.3)
- Hepatitis B virus reactivation: Monitor HBV carriers during and several months after therapy. If reactivation occurs, stop YUSIMRY and begin anti-viral therapy. (5.4)
- Demyelinating disease: Exacerbation or new onset, may occur. (5.5)
- Cytopenias, pancytopenia: Advise patients to seek immediate medical attention if symptoms develop, and consider stopping YUSIMRY. (5.6)
- Heart failure: Worsening or new onset, may occur. (5.8)
- Autoimmunity: Stop YUSIMRY if lupus-like syndrome or autoimmune hepatitis develop. (5.9)

6 ADVERSE REACTIONS

Most common adverse reactions (>10%) are: infections (e.g., upper respiratory, sinusitis), injection site reactions, headache and rash. (6.1)

To report SUSPECTED ADVERSE REACTIONS, contact Meitheal Pharmaceuticals Inc. at 1-888-808-5529 or FDA at 1-800-FDA-1088 or www.fda.gov/medwatch.

7 DRUG INTERACTIONS

- Abatacept: Increased risk of serious infection (5.1, 5.11, 7.2)
- Anakinra: Increased risk of serious infection (5.1, 5.7, 7.2)
- Live vaccines: Avoid use with YUSIMRY (5.10, 7.3)

FULL PRESCRIBING INFORMATION

WARNING: SERIOUS INFECTIONS and MALIGNANCY

SERIOUS INFECTIONS

Patients treated with adalimumab products including YUSIMRY are at increased risk for developing serious infections that may lead to hospitalization or death [see Warnings and Precautions (5.1)]. Most patients who developed these infections were taking concomitant immunosuppressants such as methotrexate or corticosteroids.

Discontinue YUSIMRY if a patient develops a serious infection or sepsis.

Reported infections include:

- Active tuberculosis (TB), including reactivation of latent TB. Patients with TB have frequently presented with disseminated or extrapulmonary disease. Test patients for latent TB before YUSIMRY use and during therapy. Initiate treatment for latent TB prior to YUSIMRY use.
- Invasive fungal infections, including histoplasmosis, coccidioidomycosis, candidiasis, aspergillosis, blastomycosis, and pneumocystosis. Patients with histoplasmosis or other invasive fungal infections may present with disseminated, rather than localized, disease. Antigen and antibody testing for histoplasmosis may be negative in some patients with active infection. Consider empiric anti-fungal therapy in patients at risk for invasive fungal infections who develop severe systemic illness.
- Bacterial, viral and other infections due to opportunistic pathogens, including Legionella and Listeria.

Carefully consider the risks and benefits of treatment with YUSIMRY prior to initiating therapy in patients with chronic or recurrent infection.

Monitor patients closely for the development of signs and symptoms of infection during and after treatment with YUSIMRY, including the possible development of TB in patients who tested negative for latent TB infection prior to initiating therapy [see Warnings and Precautions (5.1) and Adverse Reactions (6.1)].

MALIGNANCY

Lymphoma and other malignancies, some fatal, have been reported in children and adolescent patients treated with TNF blockers including adalimumab products [see Warnings and Precautions (5.2)]. Post-marketing cases of hepatosplenic T-cell lymphoma (HSTCL), a rare type of T-cell lymphoma, have been reported in patients treated with TNF blockers including adalimumab products. These cases have had a very aggressive disease course and have been fatal. The majority of reported TNF blocker cases have occurred in patients with Crohn's disease or ulcerative colitis and the majority were in adolescent and young adult males. Almost all these patients had received treatment with azathioprine or 6-mercaptopurine (6–MP) concomitantly with a TNF blocker at or prior to diagnosis. It is uncertain whether the occurrence of HSTCL is related to use of a TNF blocker or a TNF blocker in combination with these other immunosuppressants [see Warnings and Precautions (5.2)].

1 INDICATIONS AND USAGE

1.1 Rheumatoid Arthritis

YUSIMRY is indicated for reducing signs and symptoms, inducing major clinical response, inhibiting the progression of structural damage, and improving physical function in adult patients with moderately to severely active rheumatoid arthritis. YUSIMRY can be used alone or in combination with methotrexate or other non-biologic disease-modifying anti-rheumatic drugs (DMARDs).

1.2 Juvenile Idiopathic Arthritis

YUSIMRY is indicated for reducing signs and symptoms of moderately to severely active polyarticular juvenile idiopathic arthritis in patients 2 years of age and older. YUSIMRY can be used alone or in combination with methotrexate.

1.3 Psoriatic Arthritis

YUSIMRY is indicated for reducing signs and symptoms, inhibiting the progression of structural damage, and improving physical function in adult patients with active psoriatic arthritis. YUSIMRY can be used alone or in combination with non-biologic DMARDs.

1.4 Ankylosing Spondylitis

YUSIMRY is indicated for reducing signs and symptoms in adult patients with active ankylosing spondylitis.

1.5 Crohn's Disease

YUSIMRY is indicated for the treatment of moderately to severely active Crohn's disease in adults and pediatric patients 6 years of age and older.

1.6 Ulcerative Colitis

YUSIMRY is indicated for the treatment of moderately to severely active ulcerative colitis in adult patients.

Limitations of Use

The effectiveness of adalimumab products has not been established in patients who have lost response to or were intolerant to TNF blockers [see Clinical Studies (14.7)].

1.7 Plaque Psoriasis

YUSIMRY is indicated for the treatment of adult patients with moderate to severe chronic plaque psoriasis who are candidates for systemic therapy or phototherapy, and when other systemic therapies are medically less appropriate. YUSIMRY should only be administered to patients who will be closely monitored and have regular follow-up visits with a physician [see Warnings and Precautions (5)].

1.8 Hidradenitis Suppurativa

YUSIMRY is indicated for the treatment of moderate to severe hidradenitis suppurativa in adult patients.

1.9 Uveitis

YUSIMRY is indicated for the treatment of non-infectious intermediate, posterior, and panuveitis in adults.

2 DOSAGE AND ADMINISTRATION

2.1 Recommended Tuberculosis Evaluation

Prior to initiating YUSIMRY and periodically during therapy, evaluate patients for active tuberculosis and test for latent infection [see Warnings and Precautions (5.1)].

2.2 Recommended Dosage in Rheumatoid Arthritis, Psoriatic Arthritis, and Ankylosing Spondylitis

The recommended subcutaneous dosage of YUSIMRY for adult patients with rheumatoid arthritis (RA), psoriatic arthritis (PsA), or ankylosing spondylitis (AS) [see Indications and Usage (1.1, 1.3, 1.4)] is 40 mg administered every other week. Methotrexate (MTX), other non-biologic DMARDS, glucocorticoids, nonsteroidal anti-inflammatory drugs (NSAIDs), and/or analgesics may be continued during treatment with YUSIMRY. In the treatment of RA, some patients not taking concomitant MTX may derive additional benefit from increasing the dosage of YUSIMRY to 40 mg every week or 80 mg every other week.

2.3 Recommended Dosage in Juvenile Idiopathic Arthritis

The recommended subcutaneous dosage of YUSIMRY for pediatric patients 2 years of age and older with polyarticular juvenile idiopathic arthritis (JIA) [see Indications and Usage (1.2, 1.9)], based on weight, is shown below. MTX, glucocorticoids, NSAIDs, and/or analgesics may be continued during treatment with YUSIMRY.

Pediatric Weight (2 Years of Age and Older) | Recommended Dosage
30 kg (66 lbs) and greater | 40 mg every other week

There is no dosage form for YUSIMRY that allows weight-based dosing for pediatric patients below 30 kg.

Adalimumab products have not been studied in patients with polyarticular JIA less than 2 years of age or in patients with a weight below 10 kg.

2.4 Recommended Dosage in Crohn’s Disease

Subcutaneous Adult Dosage Regimen

The recommended subcutaneous dosage of YUSIMRY for adult patients with moderately to severely active Crohn’s disease (CD) is 160 mg initially on Day 1 (given in one day or split over two consecutive days), followed by 80 mg two weeks later (Day 15). Two weeks later (Day 29) begin a dosage of 40 mg every other week. Aminosalicylates and/or corticosteroids may be continued during treatment with YUSIMRY. Azathioprine, 6-mercaptopurine (6-MP) [see Warnings and Precautions (5.2)] or MTX may be continued during treatment with YUSIMRY if necessary.

Subcutaneous Pediatric Dosage Regimen

The recommended subcutaneous dosage of YUSIMRY for pediatric patients 6 years of age and older with moderately to severely active Crohn’s disease (CD), based on body weight, is shown below:

Pediatric Weight | Recommended Dosage
Pediatric Weight | Days 1 through 15 | Starting on Day 29
40 kg (88 lbs) and greater | Day 1: 160 mg (single dose or split over two consecutive days); Day 15: 80 mg | 40 mg every other week

There is no dosage form for YUSIMRY that allows weight-based dosing for pediatric patients below 40 kg.

2.5 Recommended Dosage in Ulcerative Colitis

Subcutaneous Adult Dosage Regimen

The recommended subcutaneous dosage of YUSIMRY for adult patients with moderately to severely active ulcerative colitis is 160 mg initially on Day 1 (given in one day or split over two consecutive days), followed by 80 mg two weeks later (Day 15). Two weeks later (Day 29) continue with a dosage of 40 mg every other week.

Discontinue YUSIMRY in adult patients without evidence of clinical remission by eight weeks (Day 57) of therapy. Aminosalicylates and/or corticosteroids may be continued during treatment with YUSIMRY. Azathioprine and 6-mercaptopurine (6-MP) [see Warnings and Precautions (5.2)] may be continued during treatment with YUSIMRY if necessary.

2.6 Recommended Dosage in Plaque Psoriasis or Adults with Uveitis

The recommended subcutaneous dosage of YUSIMRY for adult patients with plaque psoriasis (Ps) or uveitis (UV) [see Indications and Usage (1.7, 1.9)] is an initial dose of 80 mg, followed by 40 mg given every other week starting one week after the initial dose. The use of adalimumab products in moderate to severe chronic Ps beyond one year has not been evaluated in controlled clinical studies.

2.7 Recommended Dosage in Hidradenitis Suppurativa

Subcutaneous Adult Dosage Regimen

The recommended subcutaneous dosage of YUSIMRY for adult patients with moderate to severe hidradenitis suppurativa (HS) is an initial dose of 160 mg (given in one day or split over two consecutive days), followed by 80 mg two weeks later (Day 15). Begin 40 mg weekly or 80 mg every other week dosing two weeks later (Day 29).

2.8 General Considerations for Administration

YUSIMRY is intended for use under the guidance and supervision of a physician. A patient may self-inject YUSIMRY or a caregiver may inject YUSIMRY using either the YUSIMRY pen or prefilled syringe if a physician determines that it is appropriate, and with medical follow-up, as necessary, after proper training in subcutaneous injection technique.

YUSIMRY can be taken out of the refrigerator for 15 to 30 minutes before injecting to allow the liquid to come to room temperature. Do not remove the cap or cover while allowing it to reach room temperature. Carefully inspect the solution in the YUSIMRY pen or prefilled syringe for particulate matter and discoloration prior to subcutaneous administration. If particulates and discolorations are noted, do not use the product. YUSIMRY does not contain preservatives; therefore, discard unused portions of drug remaining from the syringe [see How Supplied/Storage and Handling (16)].

Instruct patients using the YUSIMRY pen or prefilled syringe to inject the full amount in the syringe, according to the directions provided in the Instructions for Use [see Instructions for Use].

Injections should occur at separate sites in the thigh or abdomen. Rotate injection sites and do not give injections into areas where the skin is tender, bruised, red or hard.

If a dose is missed, administer the dose as soon as possible. Thereafter, resume dosing at the regular scheduled time.

3 DOSAGE FORMS AND STRENGTHS

YUSIMRY is a clear to slightly opalescent, colorless to slightly yellow solution available as:

- Pen (YUSIMRY Pen)
  Injection: 40 mg/0.8 mL in a single-dose pen.
- Prefilled Syringe
  Injection: 40 mg/0.8 mL in a single-dose prefilled glass syringe.

4 CONTRAINDICATIONS

None.

5 WARNINGS AND PRECAUTIONS

5.1 Serious Infections

Patients treated with adalimumab products, including YUSIMRY, are at increased risk for developing serious infections involving various organ systems and sites that may lead to hospitalization or death. Opportunistic infections due to bacterial, mycobacterial, invasive fungal, viral, parasitic, or other opportunistic pathogens including aspergillosis, blastomycosis, candidiasis, coccidioidomycosis, histoplasmosis, legionellosis, listeriosis, pneumocystosis and tuberculosis have been reported with TNF blockers. Patients have frequently presented with disseminated rather than localized disease.

The concomitant use of a TNF blocker and abatacept or anakinra was associated with a higher risk of serious infections in patients with rheumatoid arthritis (RA); therefore, the concomitant use of YUSIMRY and these biologic products is not recommended in the treatment of patients with RA [see Warnings and Precautions (5.7, 5.11) and Drug Interactions (7.2)].

Treatment with YUSIMRY should not be initiated in patients with an active infection, including localized infections. Patients 65 years of age and older, patients with co-morbid conditions and/or patients taking concomitant immunosuppressants (such as corticosteroids or methotrexate), may be at greater risk of infection. Consider the risks and benefits of treatment prior to initiating therapy in patients:

- with chronic or recurrent infection;
- who have been exposed to tuberculosis;
- with a history of an opportunistic infection;
- who have resided or traveled in areas of endemic tuberculosis or endemic mycoses, such as histoplasmosis, coccidioidomycosis, or blastomycosis; or
- with underlying conditions that may predispose them to infection.

Tuberculosis

Cases of reactivation of tuberculosis and new onset tuberculosis infections have been reported in patients receiving adalimumab products, including patients who have previously received treatment for latent or active tuberculosis. Reports included cases of pulmonary and extrapulmonary (i.e., disseminated) tuberculosis. Evaluate patients for tuberculosis risk factors and test for latent infection prior to initiating YUSIMRY and periodically during therapy.

Treatment of latent tuberculosis infection prior to therapy with TNF blocking agents has been shown to reduce the risk of tuberculosis reactivation during therapy. Prior to initiating YUSIMRY, assess if treatment for latent tuberculosis is needed; and consider an induration of ≥ 5 mm a positive tuberculin skin test result, even for patients previously vaccinated with Bacille Calmette-Guerin (BCG).

Consider anti-tuberculosis therapy prior to initiation of YUSIMRY in patients with a past history of latent or active tuberculosis in whom an adequate course of treatment cannot be confirmed, and for patients with a negative test for latent tuberculosis but having risk factors for tuberculosis infection. Despite prophylactic treatment for tuberculosis, cases of reactivated tuberculosis have occurred in patients treated with adalimumab products. Consultation with a physician with expertise in the treatment of tuberculosis is recommended to aid in the decision whether initiating anti-tuberculosis therapy is appropriate for an individual patient.

Strongly consider tuberculosis in the differential diagnosis in patients who develop a new infection during YUSIMRY treatment, especially in patients who have previously or recently traveled to countries with a high prevalence of tuberculosis, or who have had close contact with a person with active tuberculosis.

Monitoring

Closely monitor patients for the development of signs and symptoms of infection during and after treatment with YUSIMRY, including the development of tuberculosis in patients who tested negative for latent tuberculosis infection prior to initiating therapy. Tests for latent tuberculosis infection may also be falsely negative while on therapy with YUSIMRY.

Discontinue YUSIMRY if a patient develops a serious infection or sepsis. For a patient who develops a new infection during treatment with YUSIMRY, closely monitor them, perform a prompt and complete diagnostic workup appropriate for an immunocompromised patient, and initiate appropriate antimicrobial therapy.

Invasive Fungal Infections

If patients develop a serious systemic illness and they reside or travel in regions where mycoses are endemic, consider invasive fungal infection in the differential diagnosis. Antigen and antibody testing for histoplasmosis may be negative in some patients with active infection. Consider appropriate empiric antifungal therapy, taking into account both the risk for severe fungal infection and the risks of antifungal therapy, while a diagnostic workup is being performed. To aid in the management of such patients, consider consultation with a physician with expertise in the diagnosis and treatment of invasive fungal infections.

5.2 Malignancies

Consider the risks and benefits of TNF-blocker treatment including YUSIMRY prior to initiating therapy in patients with a known malignancy other than a successfully treated non-melanoma skin cancer (NMSC) or when considering continuing a TNF blocker in patients who develop a malignancy.

Malignancies in Adults

In the controlled portions of clinical trials of some TNF-blockers, including adalimumab products, more cases of malignancies have been observed among TNF-blocker-treated adult subjects compared to control-treated adult subjects. During the controlled portions of 39 global adalimumab clinical trials in adult patients with rheumatoid arthritis (RA), psoriatic arthritis (PsA), ankylosing spondylitis (AS), Crohn’s disease (CD), ulcerative colitis (UC), plaque psoriasis (Ps), hidradenitis suppurativa (HS), and uveitis (UV), malignancies, other than non-melanoma (basal cell and squamous cell) skin cancer, were observed at a rate (95% confidence interval) of 0.7 (0.48, 1.03) per 100 patient-years among 7973 adalimumab-treated subjects versus a rate of 0.7 (0.41, 1.17) per 100 patient-years among 4848 control-treated subjects (median duration of treatment of 4 months for adalimumab-treated subjects and 4 months for control-treated subjects). In 52 global controlled and uncontrolled clinical trials of adalimumab in adult patients with RA, PsA, AS, CD, UC, Ps, HS, and UV, the most frequently observed malignancies, other than lymphoma and NMSC, were breast, colon, prostate, lung, and melanoma. The malignancies in adalimumab-treated subjects in the controlled and uncontrolled portions of the studies were similar in type and number to what would be expected in the general U.S. population according to the SEER database (adjusted for age, gender, and race).^1

In controlled trials of other TNF blockers in adult patients at higher risk for malignancies (i.e., subjects with COPD with a significant smoking history and cyclophosphamide-treated patients with Wegener’s granulomatosis), a greater portion of malignancies occurred in the TNF blocker group compared to the control group.

Non-Melanoma Skin Cancer

During the controlled portions of 39 global adalimumab clinical trials in adult patients with RA, PsA, AS, CD, UC, Ps, HS, and UV, the rate (95% confidence interval) of NMSC was 0.8 (0.52, 1.09) per 100 patient-years among adalimumab-treated subjects and 0.2 (0.10, 0.59) per 100
patient-years among control-treated subjects. Examine all patients, and in particular patients with a medical history of prior prolonged immunosuppressant therapy or psoriasis patients with a history of PUVA treatment for the presence of NMSC prior to and during treatment with YUSIMRY.

Lymphoma and Leukemia

In the controlled portions of clinical trials of all the TNF-blockers in adults, more cases of lymphoma have been observed among TNF-blocker-treated subjects compared to control-treated subjects. In the controlled portions of 39 global adalimumab clinical trials in adult patients with RA, PsA, AS, CD, UC, Ps, HS, and UV, 2 lymphomas occurred among 7973 adalimumab-treated subjects versus 1 among 4848 control-treated subjects. In 52 global controlled and uncontrolled clinical trials of adalimumab in adult patients with RA, PsA, AS, CD, UC, Ps, HS, and UV with a median duration of approximately 0.7 years, including 24,605 subjects and over 40,215 patient-years of adalimumab, the observed rate of lymphomas was approximately 0.11 per 100 patient-years. This is approximately 3-fold higher than expected in the general U.S. population according to the SEER database (adjusted for age, gender, and race).^1 Rates of lymphoma in clinical trials of adalimumab cannot be compared to rates of lymphoma in clinical trials of other TNF blockers and may not predict the rates observed in a broader patient population. Patients with RA and other chronic inflammatory diseases, particularly those with highly active disease and/or chronic exposure to immunosuppressant therapies, may be at a higher risk (up to several fold) than the general population for the development of lymphoma, even in the absence of TNF blockers. Post-marketing cases of acute and chronic leukemia have been reported in association with TNF-blocker use in RA and other indications. Even in the absence of TNF-blocker therapy, patients with RA may be at a higher risk (approximately 2-fold) than the general population for the development of leukemia.

Malignancies in Pediatric Patients and Young Adults

Malignancies, some fatal, have been reported among children, adolescents, and young adults who received treatment with TNF-blockers (initiation of therapy ≤ 18 years of age), of which YUSIMRY is a member. Approximately half the cases were lymphomas, including Hodgkin's and non-Hodgkin's lymphoma. The other cases represented a variety of different malignancies and included rare malignancies usually associated with immunosuppression and malignancies that are not usually observed in children and adolescents. The malignancies occurred after a median of 30 months of therapy (range 1 to 84 months). Most of the patients were receiving concomitant immunosuppressants. These cases were reported post-marketing and are derived from a variety of sources including registries and spontaneous postmarketing reports.

Postmarketing cases of hepatosplenic T-cell lymphoma (HSTCL), a rare type of T-cell lymphoma, have been reported in patients treated with TNF blockers including adalimumab products. These cases have had a very aggressive disease course and have been fatal. The majority of reported TNF blocker cases have occurred in patients with Crohn's disease or ulcerative colitis and the majority were in adolescent and young adult males. Almost all of these patients had received treatment with the immunosuppressants azathioprine or 6-mercaptopurine (6–MP) concomitantly with a TNF blocker at or prior to diagnosis. It is uncertain whether the occurrence of HSTCL is related to use of a TNF blocker or a TNF blocker in combination with these other immunosuppressants. The potential risk with the combination of azathioprine or 6-mercaptopurine and YUSIMRY should be carefully considered.

5.3 Hypersensitivity Reactions

Anaphylaxis and angioneurotic edema have been reported following administration of adalimumab products. If an anaphylactic or other serious allergic reaction occurs, immediately discontinue administration of YUSIMRY and institute appropriate therapy. In clinical trials of adalimumab hypersensitivity reactions (e.g., rash, anaphylactoid reaction, fixed drug reaction, non-specified drug reaction, urticaria) have been observed.

5.4 Hepatitis B Virus Reactivation

Use of TNF blockers, including YUSIMRY, may increase the risk of reactivation of hepatitis B virus (HBV) in patients who are chronic carriers of this virus. In some instances, HBV reactivation occurring in conjunction with TNF blocker therapy has been fatal. The majority of these reports have occurred in patients concomitantly receiving other medications that suppress the immune system, which may also contribute to HBV reactivation. Evaluate patients at risk for HBV infection for prior evidence of HBV infection before initiating TNF blocker therapy. Exercise caution in prescribing TNF blockers for patients identified as carriers of HBV. Adequate data are not available on the safety or efficacy of treating patients who are carriers of HBV with anti-viral therapy in conjunction with TNF blocker therapy to prevent HBV reactivation. For patients who are carriers of HBV and require treatment with TNF blockers, closely monitor such patients for clinical and laboratory signs of active HBV infection throughout therapy and for several months following termination of therapy. In patients who develop HBV reactivation, stop YUSIMRY and initiate effective anti-viral therapy with appropriate supportive treatment. The safety of resuming TNF blocker therapy after HBV reactivation is controlled is not known. Therefore, exercise caution when considering resumption of YUSIMRY therapy in this situation and monitor patients closely.

5.5 Neurologic Reactions

Use of TNF blocking agents, including adalimumab products, has been associated with rare cases of new onset or exacerbation of clinical symptoms and/or radiographic evidence of central nervous system demyelinating disease, including multiple sclerosis (MS) and optic neuritis, and peripheral demyelinating disease, including Guillain-Barré syndrome. Exercise caution in considering the use of YUSIMRY in patients with pre-existing or recent-onset central or peripheral nervous system demyelinating disorders; discontinuation of YUSIMRY should be considered if any of these disorders develop. There is a known association between intermediate uveitis and central demyelinating disorders.

5.6 Hematological Reactions

Rare reports of pancytopenia including aplastic anemia have been reported with TNF blocking agents. Adverse reactions of the hematologic system, including medically significant cytopenia (e.g., thrombocytopenia, leukopenia) have been infrequently reported with adalimumab products. The causal relationship of these reports to adalimumab products remains unclear. Advise all patients to seek immediate medical attention if they develop signs and symptoms suggestive of blood dyscrasias or infection (e.g., persistent fever, bruising, bleeding, pallor) while on YUSIMRY. Consider discontinuation of YUSIMRY therapy in patients with confirmed significant hematologic abnormalities.

5.7 Increased Risk of Infection When Used with Anakinra

Concurrent use of anakinra (an interleukin-1 antagonist) and another TNF-blocker, was associated with a greater proportion of serious infections and neutropenia and no added benefit compared with the TNF-blocker alone in patients with RA. Therefore, the combination of YUSIMRY and anakinra is not recommended [see Drug Interactions (7.2)].

5.8 Heart Failure

Cases of worsening congestive heart failure (CHF) and new onset CHF have been reported with TNF blockers. Cases of worsening CHF have also been observed with adalimumab products. Adalimumab products have not been formally studied in patients with CHF; however, in clinical trials of another TNF blocker, a higher rate of serious CHF-related adverse reactions was observed. Exercise caution when using YUSIMRY in patients who have heart failure and monitor them carefully.

5.9 Autoimmunity

Treatment with adalimumab products may result in the formation of autoantibodies and, rarely, in the development of a lupus-like syndrome or autoimmune hepatitis [see Adverse Reactions (6.1, 6.3)]. If a patient develops symptoms and findings suggestive of a lupus-like syndrome or autoimmune hepatitis following treatment with YUSIMRY, discontinue treatment and evaluate the patient.

5.10 Immunizations

In a placebo-controlled clinical trial of patients with RA, no difference was detected in anti- pneumococcal antibody response between adalimumab and placebo treatment groups when the pneumococcal polysaccharide vaccine and influenza vaccine were administered concurrently with adalimumab. Similar proportions of subjects developed protective levels of anti-influenza antibodies between adalimumab and placebo treatment groups; however, titers in aggregate to influenza antigens were moderately lower in patients receiving adalimumab. The clinical significance of this is unknown. Patients on YUSIMRY may receive concurrent vaccinations, except for live vaccines. No data are available on the secondary transmission of infection by live vaccines in patients receiving adalimumab products.

It is recommended that pediatric patients, if possible, be brought up to date with all immunizations in agreement with current immunization guidelines prior to initiating YUSIMRY therapy. Patients on YUSIMRY may receive concurrent vaccinations, except for live vaccines.

The safety of administering live or live-attenuated vaccines in infants exposed to adalimumab products in utero is unknown. Risks and benefits should be considered prior to vaccinating (live or live-attenuated) exposed infants [see Use in Specific Populations (8.1, 8.4)].

5.11 Increased Risk of Infection When Used with Abatacept

In controlled trials, the concurrent administration of TNF-blockers and abatacept was associated with a greater proportion of serious infections than the use of a TNF-blocker alone; the combination therapy, compared to the use of a TNF-blocker alone, has not demonstrated improved clinical benefit in the treatment of RA. Therefore, the combination of abatacept with TNF-blockers including YUSIMRY is not recommended [see Drug Interactions (7.2)].

6 ADVERSE REACTIONS

The following clinically significant adverse reactions are described elsewhere in the labeling:

- Serious Infections [see Warnings and Precautions (5.1)]
- Malignancies [see Warnings and Precautions (5.2)]
- Hypersensitivity Reactions [see Warnings and Precautions (5.3)]
- Hepatitis B Virus Reactivation [see Warnings and Precautions (5.4)]
- Neurologic Reactions [see Warnings and Precautions (5.5)]
- Hematological Reactions [see Warnings and Precautions (5.6)]
- Heart Failure [see Warnings and Precautions (5.8)]
- Autoimmunity [see Warnings and Precautions (5.9)]

6.1 Clinical Trials Experience

Because clinical trials are conducted under widely varying conditions, adverse reaction rates observed in the clinical trials of a drug cannot be directly compared to rates in the clinical trials of another drug and may not reflect the rates observed in practice.

The most common adverse reaction with adalimumab was injection site reactions. In placebo- controlled trials, 20% of subjects treated with adalimumab developed injection site reactions (erythema and/or itching, hemorrhage, pain or swelling), compared to 14% of subjects receiving placebo. Most injection site reactions were described as mild and generally did not necessitate drug discontinuation.

The proportion of subjects who discontinued treatment due to adverse reactions during the double-blind, placebo-controlled portion of studies in subjects with RA (i.e., Studies RA-I, RA-II, RA-III and RA-IV) was 7% for subjects taking adalimumab and 4% for placebo-treated subjects. The most common adverse reactions leading to discontinuation of adalimumab in these RA studies were clinical flare reaction (0.7%), rash (0.3%) and pneumonia (0.3%).

Infections

In the controlled portions of the 39 global adalimumab clinical trials in adult subjects with RA, PsA, AS, CD, UC, Ps, HS, and UV, the rate of serious infections was 4.3 per 100 patient-years in 7973 adalimumab-treated subjects versus a rate of 2.9 per 100 patient-years in 4848 control-treated subjects. Serious infections observed included pneumonia, septic arthritis, prosthetic and post-surgical infections, erysipelas, cellulitis, diverticulitis, and pyelonephritis [see Warnings and Precautions (5.1)].

Tuberculosis and Opportunistic Infections

In 52 global controlled and uncontrolled clinical trials in RA, PsA, AS, CD, UC, Ps, HS and UV that included 24,605 adalimumab-treated subjects, the rate of reported active tuberculosis was 0.20 per 100 patient-years and the rate of positive PPD conversion was 0.09 per 100 patient-years. In a subgroup of 10,113 U.S. and Canadian adalimumab-treated subjects, the rate of reported active TB was 0.05 per 100 patient-years and the rate of positive PPD conversion was 0.07 per 100 patient-years. These trials included reports of miliary, lymphatic, peritoneal, and pulmonary TB. Most of the TB cases occurred within the first eight months after initiation of therapy and may reflect recrudescence of latent disease. In these global clinical trials, cases of serious opportunistic infections have been reported at an overall rate of 0.05 per 100 patient-years. Some cases of serious opportunistic infections and TB have been fatal [see Warnings and Precautions (5.1)].

Autoantibodies

In the rheumatoid arthritis controlled trials, 12% of subjects treated with adalimumab and 7% of placebo-treated subjects that had negative baseline ANA titers developed positive titers at Week 24. Two subjects out of 3046 treated with adalimumab developed clinical signs suggestive of new-onset lupus-like syndrome. The subjects improved following discontinuation of therapy. No subjects developed lupus nephritis or central nervous system symptoms. The impact of long-term treatment with adalimumab products on the development of autoimmune diseases is unknown.

Liver Enzyme Elevations

There have been reports of severe hepatic reactions including acute liver failure in subjects receiving TNF-blockers. In controlled Phase 3 trials of adalimumab (40 mg SC every other week) in subjects with RA, PsA, and AS with control period duration ranging from 4 to 104 weeks, ALT elevations ≥ 3 x ULN occurred in 3.5% of adalimumab-treated subjects and 1.5% of control-treated subjects. Since many of these subjects in these trials were also taking medications that cause liver enzyme elevations (e.g., NSAIDS, MTX), the relationship between adalimumab and the liver enzyme elevations is not clear. In a controlled Phase 3 trial of adalimumab in subjects with polyarticular JIA who were 4 to 17 years, ALT elevations ≥ 3 x ULN occurred in 4.4% of adalimumab-treated subjects and 1.5% of control-treated subjects (ALT more common than AST); liver enzyme test elevations were more frequent among those treated with the combination of adalimumab and MTX than those treated with adalimumab alone. In general, these elevations did not lead to discontinuation of adalimumab treatment. No ALT elevations ≥ 3 x ULN occurred in the open-label study of adalimumab in subjects with polyarticular JIA who were 2 to <4 years.

In controlled Phase 3 trials of adalimumab (initial doses of 160 mg and 80 mg, or 80 mg and 40 mg on Days 1 and 15, respectively, followed by 40 mg every other week) in adult subjects with Crohn’s Disease with a control period duration ranging from 4 to 52 weeks, ALT elevations ≥ 3 x ULN occurred in 0.9% of adalimumab-treated subjects and 0.9% of control-treated subjects. In the Phase 3 trial of adalimumab in pediatric subjects with Crohn’s disease which evaluated efficacy and safety of two body weight based maintenance dose regimens following body weight based induction therapy up to 52 weeks of treatment, ALT elevations ≥ 3 x ULN occurred in 2.6% (5/192) of subjects, of whom 4 were receiving concomitant immunosuppressants at baseline; none of these subjects discontinued due to abnormalities in ALT tests. In controlled Phase 3 trials of adalimumab (initial doses of 160 mg and 80 mg on Days 1 and 15 respectively, followed by 40 mg every other week) in adult subjects with UC with control period duration ranging from 1 to 52 weeks, ALT elevations ≥3 x ULN occurred in 1.5% of adalimumab-treated subjects and 1.0% of control-treated subjects. In controlled Phase 3 trials of adalimumab (initial dose of 80 mg then 40 mg every other week) in subjects with Ps with control period duration ranging from 12 to 24 weeks, ALT elevations ≥ 3 x ULN occurred in 1.8% of adalimumab-treated subjects and 1.8% of control-treated subjects. In controlled trials of adalimumab (initial doses of 160 mg at Week 0 and 80 mg at Week 2, followed by 40 mg every week starting at Week 4), in subjects with HS with a control period duration ranging from 12 to 16 weeks, ALT elevations ≥ 3 x ULN occurred in 0.3% of adalimumab-treated subjects and 0.6% of control-treated subjects. In controlled trials of adalimumab (initial doses of 80 mg at Week 0 followed by 40 mg every other week starting at Week 1) in adult subjects with uveitis with an exposure of 165.4 PYs and 119.8 PYs in adalimumab-treated and control-treated subjects, respectively, ALT elevations ≥ 3 x ULN occurred in 2.4% of adalimumab-treated subjects and 2.4% of control-treated subjects.

Other Adverse Reactions

Rheumatoid Arthritis Clinical Studies

The data described below reflect exposure to adalimumab in 2468 subjects, including 2073 exposed for 6 months, 1497 exposed for greater than one year and 1380 in adequate and well-controlled studies (Studies RA-I, RA-II, RA-III, and RA-IV). Adalimumab was studied primarily in placebo-controlled trials and in long-term follow up studies for up to 36 months duration. The population had a mean age of 54 years, 77% were female, 91% were Caucasian and had moderately to severely active rheumatoid arthritis. Most subjects received 40 mg adalimumab every other week [see Clinical Studies (14.1)].

Table 1 summarizes reactions reported at a rate of at least 5% in subjects treated with adalimumab 40 mg every other week compared to placebo and with an incidence higher than placebo. In Study RA-III, the types and frequencies of adverse reactions in the second year open-label extension were similar to those observed in the one-year double-blind portion.

Table 1. Adverse Reactions Reported by ≥ 5% of Subjects Treated with Adalimumab During Placebo-Controlled Period of Pooled RA Studies (Studies RA-I, RA-II, RA-III, and RA-IV)
 | Adalimumab 40 mg subcutaneous Every Other Week (N=705) | Placebo (N=690)
Adverse Reaction (Preferred Term)
Respiratory
Upper respiratory infection | 17% | 13%
Sinusitis | 11% | 9%
Flu syndrome | 7% | 6%
Gastrointestinal
Nausea | 9% | 8%
Abdominal pain | 7% | 4%
Laboratory Tests*
Laboratory test abnormal | 8% | 7%
Hypercholesterolemia | 6% | 4%
Hyperlipidemia | 7% | 5%
Hematuria | 5% | 4%
Alkaline phosphatase increased | 5% | 3%
Other
Headache | 12% | 8%
Rash | 12% | 6%
Accidental injury | 10% | 8%
Injection site reaction** | 8% | 1%
Back pain | 6% | 4%
Urinary tract infection | 8% | 5%
Hypertension | 5% | 3%
* Laboratory test abnormalities were reported as adverse reactions in European trials
** Does not include injection site erythema, itching, hemorrhage, pain or swelling

Less Common Adverse Reactions in Rheumatoid Arthritis Clinical Studies

Other infrequent serious adverse reactions that do not appear in the Warnings and Precautions or Adverse Reactions sections that occurred at an incidence of less than 5% in adalimumab-treated subjects in RA studies (RA-I, RA-II, RA-III, and RA-IV) were:

- Body as a Whole: Pain in extremity, pelvic pain, surgery, thorax pain
- Cardiovascular System: Arrhythmia, atrial fibrillation, chest pain, coronary artery disorder, heart arrest, hypertensive encephalopathy, myocardial infarct, palpitation, pericardial effusion, pericarditis, syncope, tachycardia
- Digestive System: Cholecystitis, cholelithiasis, esophagitis, gastroenteritis, gastrointestinal hemorrhage, hepatic necrosis, vomiting
- Endocrine System: Parathyroid disorder
- Hemic and Lymphatic System: Agranulocytosis, polycythemia
- Metabolic and Nutritional Disorders: Dehydration, healing abnormal, ketosis, paraproteinemia, peripheral edema
- Musculo-Skeletal System: Arthritis, bone disorder, bone fracture (not spontaneous), bone necrosis, joint disorder, muscle cramps, myasthenia, pyogenic arthritis, synovitis, tendon disorder
- Neoplasia: Adenoma
- Nervous System: Confusion, paresthesia, subdural hematoma, tremor
- Respiratory System: Asthma, bronchospasm, dyspnea, lung function decreased, pleural effusion
- Special Senses: Cataract
- Thrombosis: Thrombosis leg
- Urogenital System: Cystitis, kidney calculus, menstrual disorder

Juvenile Idiopathic Arthritis Clinical Studies

In general, the adverse reactions in the adalimumab-treated subjects in the polyarticular juvenile idiopathic arthritis (JIA) trials (Studies JIA-I and JIA-II) [see Clinical Studies (14.2)] were similar in frequency and type to those seen in adult subjects [see Warnings and Precautions (5), Adverse Reactions (6)]. Important findings and differences from adults are discussed in the following paragraphs.

In Study JIA-I, adalimumab was studied in 171 subjects who were 4 to 17 years of age, with polyarticular JIA. Severe adverse reactions reported in the study included neutropenia, streptococcal pharyngitis, increased aminotransferases, herpes zoster, myositis, metrorrhagia, and appendicitis. Serious infections were observed in 4% of subjects within approximately 2 years of initiation of treatment with adalimumab and included cases of herpes simplex, pneumonia, urinary tract infection, pharyngitis, and herpes zoster.

In Study JIA-I, 45% of subjects experienced an infection while receiving adalimumab with or without concomitant MTX in the first 16 weeks of treatment. The types of infections reported in adalimumab-treated subjects were generally similar to those commonly seen in polyarticular JIA subjects who are not treated with TNF blockers. Upon initiation of treatment, the most common adverse reactions occurring in this population treated with adalimumab were injection site pain and injection site reaction (19% and 16%, respectively). A less commonly reported adverse event in subjects receiving adalimumab was granuloma annulare which did not lead to discontinuation of adalimumab treatment.

In the first 48 weeks of treatment in Study JIA-I, non-serious hypersensitivity reactions were seen in approximately 6% of subjects and included primarily localized allergic hypersensitivity reactions and allergic rash.

In Study JIA-I, 10% of subjects treated with adalimumab who had negative baseline anti-dsDNA antibodies developed positive titers after 48 weeks of treatment. No subject developed clinical signs of autoimmunity during the clinical trial.

Approximately 15% of subjects treated with adalimumab developed mild-to-moderate elevations of creatine phosphokinase (CPK) in Study JIA-I. Elevations exceeding 5 times the upper limit of normal were observed in several subjects. CPK concentrations decreased or returned to normal in all subjects. Most subjects were able to continue adalimumab without interruption.

In Study JIA-II, adalimumab was studied in 32 subjects who were 2 to <4 years of age or 4 years of age and older weighing <15 kg with polyarticular JIA. The safety profile for this population was similar to the safety profile seen in subjects 4 to 17 years of age with polyarticular JIA.

In Study JIA-II, 78% of subjects experienced an infection while receiving adalimumab. These included nasopharyngitis, bronchitis, upper respiratory tract infection, otitis media, and were mostly mild to moderate in severity. Serious infections were observed in 9% of subjects receiving adalimumab in the study and included dental caries, rotavirus gastroenteritis, and varicella.

In Study JIA-II, non-serious allergic reactions were observed in 6% of subjects and included intermittent urticaria and rash, which were all mild in severity.

Psoriatic Arthritis and Ankylosing Spondylitis Clinical Studies

Adalimumab has been studied in 395 subjects with psoriatic arthritis (PsA) in two placebo-controlled trials and in an open label study and in 393 subjects with ankylosing spondylitis (AS) in two placebo-controlled studies [see Clinical Studies (14.3, 14.4)]. The safety profile for subjects with PsA and AS treated with adalimumab 40 mg every other week was similar to the safety profile seen in subjects with RA, adalimumab Studies RA-I through IV.

Crohn's Disease Clinical Studies

Adults: The safety profile of adalimumab in 1478 adult subjects with Crohn’s disease from four placebo-controlled and two open-label extension studies [see Clinical Studies (14.5)] was similar to the safety profile seen in subjects with RA.

Pediatric Patients 6 Years to 17 Years: The safety profile of adalimumab in 192 pediatric subjects from one double-blind study (Study PCD-I) and one open-label extension study [see Clinical Studies (14.6)] was similar to the safety profile seen in adult subjects with Crohn’s disease.

During the 4-week open label induction phase of Study PCD-I, the most common adverse reactions occurring in the pediatric population treated with adalimumab were injection site pain and injection site reaction (6% and 5%, respectively).

A total of 67% of children experienced an infection while receiving adalimumab in Study PCD-I. These included upper respiratory tract infection and nasopharyngitis.

A total of 5% of children experienced a serious infection while receiving adalimumab in Study PCD-I. These included viral infection, device related sepsis (catheter), gastroenteritis, H1N1 influenza, and disseminated histoplasmosis.

In Study PCD-I, allergic reactions were observed in 5% of children which were all non-serious and were primarily localized reactions.

Ulcerative Colitis Clinical Studies

Adults: The safety profile of adalimumab in 1010 adult subjects with ulcerative colitis (UC) from two placebo-controlled studies and one open-label extension study [see Clinical Studies (14.7)] was similar to the safety profile seen in subjects with RA.

Plaque Psoriasis Clinical Studies

Adalimumab has been studied in 1696 subjects with plaque psoriasis (Ps) in placebo-controlled and open-label extension studies [see Clinical Studies (14.8)]. The safety profile for subjects with Ps treated with adalimumab was similar to the safety profile seen in subjects with RA with the following exceptions. In the placebo-controlled portions of the clinical trials in Ps subjects, adalimumab-treated subjects had a higher incidence of arthralgia when compared to controls (3% vs. 1%).

Hidradenitis Suppurativa Clinical Studies

Adalimumab has been studied in 727 subjects with hidradenitis suppurativa (HS) in three placebo-controlled studies and one open-label extension study [see Clinical Studies (14.9)]. The safety profile for subjects with HS treated with adalimumab weekly was consistent with the known safety profile of adalimumab.

Flare of HS, defined as ≥25% increase from baseline in abscesses and inflammatory nodule counts and with a minimum of 2 additional lesions, was documented in 22 (22%) of the 100 subjects who were withdrawn from adalimumab treatment following the primary efficacy timepoint in two studies.

Uveitis Clinical Studies

Adalimumab has been studied in 464 adult subjects with uveitis (UV) in placebo-controlled and open-label extension studies [see Clinical Studies (14.10)]. The safety profile for subjects with UV treated with adalimumab was similar to the safety profile seen in subjects with RA.

6.2 Immunogenicity

The observed incidence of anti-drug antibodies is highly dependent on the sensitivity and specificity of the assay. Differences in assay methods preclude meaningful comparisons of the incidence of anti-drug antibodies in the studies described below with the incidence of anti-drug antibodies in other studies, including those of adalimumab or of other adalimumab products. There are two assays that have been used to measure anti-adalimumab antibodies. With the ELISA, antibodies to adalimumab could be detected only when serum adalimumab concentrations were < 2 mcg/mL. The ECL assay can detect anti-adalimumab antibody titers independent of adalimumab concentrations in the serum samples. The incidence of anti-adalimumab antibody (AAA) development in patients treated with adalimumab are presented in Table 2.

Table 2. Anti-Adalimumab Antibody Development Determined by ELISA and ECL Assay in Patients Treated with adalimumab
Indications |  | Study Duration | Anti-Adalimumab Antibody Incidence by Elisa (n/N) |  | Anti-Adalimumab Antibody Incidence by ECL Assay (n/N)
 |  |  | In all patients who received adalimumab | In patients with serum adalimumab concentrations < 2 mcg/mL
Rheumatoid Arthritisa |  | 6 to 12 months | 5% (58/1062) | NR | NA
Juvenile Idiopathic Arthritis (JIA) | 4 to 17 years of ageb | 48 weeks | 16% (27/171) | NR | NA
Juvenile Idiopathic Arthritis (JIA) | 2 to 4 years of age or ≥ 4 years of age and weighing < 15 kg | 24 weeks | 7% (1/15)c | NR | NA
Psoriatic Arthritisd |  | 48 weekse | 13% (24/178) | NR | NA
Ankylosing Spondylitis |  | 24 weeks | 9% (16/185) | NR | NA
Adult Crohn's Disease |  | 56 weeks | 3% (7/269) | 8% (7/86) | NA
Pediatric Crohn's Disease |  | 52 weeks | 3% (6/182) | 10% (6/58) | NA
Adult Ulcerative Colitis |  | 52 weeks | 5% (19/360) | 21% (19/92) | NA
Plaque Psoriasisf |  | Up to 52 weeksg | 8% (77/920) | 21% (77/372) | NA
Hidradenitis Suppurativa |  | 36 weeks | 7% (30/461) | 28% (58/207)h | 61% (272/445)i
Non-infectious Uveitis |  | 52 weeks | 5% (12/249) | 21% (12/57) | 40% (99/249)j

n: number of patients with anti-adalimumab antibody; NR: not reported; NA: Not applicable (not performed)
a In patients receiving concomitant methotrexate (MTX), the incidence of anti-adalimumab antibody was 1% compared to 12% with adalimumab monotherapy
b In patients receiving concomitant MTX, the incidence of anti-adalimumab antibody was 6% compared to 26% with adalimumab monotherapy
c This patient received concomitant MTX
d In patients receiving concomitant MTX, the incidence of antibody development was 7% compared to 1% in RA
e Subjects enrolled after completing 2 previous studies of 24 weeks or 12 weeks of treatments.
f In plaque psoriasis patients who were on adalimumab monotherapy and subsequently withdrawn from the treatment, the rate of antibodies to adalimumab after retreatment was similar to the rate observed prior to withdrawal
g One 12-week Phase 2 study and one 52-week Phase 3 study
h Among subjects in the 2 Phase 3 studies who stopped adalimumab treatment for up to 24 weeks and in whom adalimumab serum levels subsequently declined to <2 mcg/mL (approximately 22% of total subjects studied)
i No apparent association between antibody development and safety was observed
j No correlation of antibody development to safety or efficacy outcomes was observed

Rheumatoid Arthritis and Psoriatic Arthritis: Subjects in Studies RA-I, RA-II, and RA-III were tested at multiple time points for antibodies to adalimumab using the ELISA during the 6-to 12-month period. No apparent correlation of antibody development to adverse reactions was observed. With monotherapy, subjects receiving every other week dosing may develop antibodies more frequently than those receiving weekly dosing. In subjects receiving the recommended dosage of 40 mg every other week as monotherapy, the ACR 20 response was lower among antibody-positive subjects than among antibody-negative subjects. The long-term immunogenicity of adalimumab products is unknown.

6.3 Postmarketing Experience

The following adverse reactions have been identified during post-approval use of adalimumab products. Because these reactions are reported voluntarily from a population of uncertain size, it is not always possible to reliably estimate their frequency or establish a causal relationship to adalimumab products exposure.

Gastrointestinal disorders: Diverticulitis, large bowel perforations including perforations associated with diverticulitis and appendiceal perforations associated with appendicitis, pancreatitis

General disorders and administration site conditions: Pyrexia

Hepato-biliary disorders: Liver failure, hepatitis, autoimmune hepatitis

Immune system disorders: Sarcoidosis

Neoplasms benign, malignant and unspecified (including cysts and polyps): Merkel Cell Carcinoma (neuroendocrine carcinoma of the skin)

Nervous system disorders: Demyelinating disorders (e.g., optic neuritis, Guillain-Barré syndrome), cerebrovascular accident

Respiratory disorders: Interstitial lung disease, including pulmonary fibrosis, pulmonary embolism

Skin reactions: Stevens Johnson Syndrome, cutaneous vasculitis, erythema multiforme, new or worsening psoriasis (all sub-types including pustular and palmoplantar), alopecia, lichenoid skin reaction

Vascular disorders: Systemic vasculitis, deep vein thrombosis

7 DRUG INTERACTIONS

7.1 Methotrexate

Adalimumab has been studied in rheumatoid arthritis (RA) patients taking concomitant methotrexate (MTX). Although MTX reduced the apparent adalimumab clearance, the data do not suggest the need for dose adjustment of either YUSIMRY or MTX [see Clinical Pharmacology (12.3)].

7.2 Biological Products

In clinical studies in patients with RA, an increased risk of serious infections has been observed with the combination of TNF blockers with anakinra or abatacept, with no added benefit; therefore, use of YUSIMRY with abatacept or anakinra is not recommended in patients with RA [see Warnings and Precautions (5.7, 5.11)]. A higher rate of serious infections has also been observed in patients with RA treated with rituximab who received subsequent treatment with a TNF blocker. There is insufficient information regarding the concomitant use of YUSIMRY and other biologic products for the treatment of RA, PsA, AS, CD, UC, Ps HS, and UV. Concomitant administration of YUSIMRY with other biologic DMARDS (e.g., anakinra and abatacept) or other TNF blockers is not recommended based upon the possible increased risk for infections and other potential pharmacological interactions.

7.3 Live Vaccines

Avoid the use of live vaccines with YUSIMRY [see Warnings and Precautions (5.10)].

7.4 Cytochrome P450 Substrates

The formation of CYP450 enzymes may be suppressed by increased concentrations of cytokines (e.g., TNFα, IL-6) during chronic inflammation. It is possible for products that antagonize cytokine activity, such as adalimumab products, to influence the formation of CYP450 enzymes. Upon initiation or discontinuation of YUSIMRY in patients being treated with CYP450 substrates with a narrow therapeutic index, monitoring of the effect (e.g., warfarin) or drug concentration (e.g., cyclosporine or theophylline) is recommended and the individual dose of the drug product may be adjusted as needed.

8 USE IN SPECIFIC POPULATIONS

8.1 Pregnancy

Risk Summary

Available studies with use of adalimumab during pregnancy do not reliably establish an association between adalimumab and major birth defects. Clinical data are available from the Organization of Teratology Information Specialists (OTIS)/MotherToBaby Pregnancy Registry in pregnant women with rheumatoid arthritis (RA) or Crohn's disease (CD) treated with adalimumab. Registry results showed a rate of 10% for major birth defects with first trimester use of adalimumab in pregnant women with RA or CD and a rate of 7.5% for major birth defects in the disease-matched comparison cohort. The lack of pattern of major birth defects is reassuring and differences between exposure groups may have impacted the occurrence of birth defects (see Data).

Adalimumab is actively transferred across the placenta during the third trimester of pregnancy and may affect immune response in the in-utero exposed infant (see Clinical Considerations). In an embryo-fetal perinatal development study conducted in cynomolgus monkeys, no fetal harm or malformations were observed with intravenous administration of adalimumab during organogenesis and later in gestation, at doses that produced exposures up to approximately 373 times the maximum recommended human dose (MRHD) of 40 mg subcutaneous without methotrexate (see Data).

The estimated background risk of major birth defects and miscarriage for the indicated populations is unknown. All pregnancies have a background risk of birth defect, loss, or other adverse outcomes. In the U.S. general population, the estimated background risk of major birth defects and miscarriage in clinically recognized pregnancies is 2-4% and 15-20%, respectively.

Clinical Considerations

Disease-associated maternal and embryo/fetal risk

Published data suggest that the risk of adverse pregnancy outcomes in women with RA or inflammatory bowel disease (IBD) is associated with increased disease activity. Adverse pregnancy outcomes include preterm delivery (before 37 weeks of gestation), low birth weight (less than 2500 g) infants, and small for gestational age at birth.

Fetal/Neonatal Adverse Reactions

Monoclonal antibodies are increasingly transported across the placenta as pregnancy progresses, with the largest amount transferred during the third trimester (see Data). Risks and benefits should be considered prior to administering live or live-attenuated vaccines to infants exposed to adalimumab products in utero [see Use in Specific Populations (8.4)].

Data

Human Data

A prospective cohort pregnancy exposure registry conducted by OTIS/MotherToBaby in the U.S. and Canada between 2004 and 2016 compared the risk of major birth defects in live-born infants of 221 women (69 RA, 152 CD) treated with adalimumab during the first trimester and 106 women (74 RA, 32 CD) not treated with adalimumab.

The proportion of major birth defects among live-born infants in the adalimumab-treated and untreated cohorts was 10% (8.7% RA, 10.5% CD) and 7.5% (6.8% RA, 9.4% CD), respectively. The lack of pattern of major birth defects is reassuring and differences between exposure groups may have impacted the occurrence of birth defects. This study cannot reliably establish whether there is an association between adalimumab and major birth defects because of methodological limitations of the registry, including small sample size, the voluntary nature of the study, and the non-randomized design.

In an independent clinical study conducted in ten pregnant women with IBD treated with adalimumab, adalimumab concentrations were measured in maternal serum as well as in cord blood (n=10) and infant serum (n=8) on the day of birth. The last dose of adalimumab was given between 1 and 56 days prior to delivery. Adalimumab concentrations were 0.16-19.7 mcg/mL in cord blood, 4.28-17.7 mcg/mL in infant serum, and 0-16.1 mcg/mL in maternal serum. In all but one case, the cord blood concentration of adalimumab was higher than the maternal serum concentration, suggesting adalimumab actively crosses the placenta. In addition, one infant had serum concentrations at each of the following: 6 weeks (1.94 mcg/mL), 7 weeks (1.31 mcg/mL), 8 weeks (0.93 mcg/mL), and 11 weeks (0.53 mcg/mL), suggesting adalimumab can be detected in the serum of infants exposed in utero for at least 3 months from birth.

Animal Data

In an embryo-fetal perinatal development study, pregnant cynomolgus monkeys received adalimumab from gestation days 20 to 97 at doses that produced exposures up to 373 times that achieved with the MRHD without methotrexate (on an AUC basis with maternal IV doses up to 100 mg/kg/week). Adalimumab did not elicit harm to the fetuses or malformations.

8.2 Lactation

Risk Summary

Limited data from case reports in the published literature describe the presence of adalimumab in human milk at infant doses of 0.1% to 1% of the maternal serum concentration. Published data suggest that the systemic exposure to a breastfed infant is expected to be low because adalimumab is a large molecule and is degraded in the gastrointestinal tract. However, the effects of local exposure in the gastrointestinal tract are unknown. There are no reports of adverse effects of adalimumab products on the breastfed infant and no effects on milk production. The developmental and health benefits of breastfeeding should be considered along with the mother's clinical need for YUSIMRY and any potential adverse effects on the breastfed child from YUSIMRY or from the underlying maternal condition.

8.4 Pediatric Use

The safety and effectiveness of YUSIMRY have not been established in pediatric patients with psoriatic arthritis, ankylosing spondylitis, or plaque psoriasis.

The safety and effectiveness of YUSIMRY have been established for:

- reducing signs and symptoms of moderately to severely active polyarticular JIA in pediatric patients 2 years of age and older.
- the treatment of moderately to severely active Crohn's disease in pediatric patients 6 years of age and older.

Pediatric assessments for YUSIMRY demonstrate that YUSIMRY is safe and effective for pediatric patients in indications for which Humira (adalimumab) is approved. However, YUSIMRY is not approved for such indications due to marketing exclusivity for Humira (adalimumab).

Due to their inhibition of TNFα, adalimumab products administered during pregnancy could affect immune response in the in utero-exposed newborn and infant. Data from eight infants exposed to adalimumab in utero suggest adalimumab crosses the placenta [see Use in Specific Populations (8.1)]. The clinical significance of elevated adalimumab concentrations in infants is unknown. The safety of administering live or live-attenuated vaccines in exposed infants is unknown. Risks and benefits should be considered prior to vaccinating (live or live-attenuated) exposed infants.

Post-marketing cases of lymphoma, including hepatosplenic T-cell lymphoma and other malignancies, some fatal, have been reported among children, adolescents, and young adults who received treatment with TNF-blockers including adalimumab products [see Warnings and Precautions (5.2)].

Juvenile Idiopathic Arthritis

The safety and effectiveness of YUSIMRY for the treatment of moderately to severely active polyarticular JIA have been established in pediatric patients 2 years of age and older. Use for this indication is supported by evidence from an adequate and well-controlled study (Study JIA) of adalimumab in patients 4 to 17 years of age [see Clinical Studies (14.2)] and a safety study (Study JIA-II) of adalimumab in patients 2 to <4 years of age where the safety profile was similar to patients 4 to 17 years of age [see Adverse Reactions (6.1)]. Adalimumab products have not been studied in patients with polyarticular JIA less than 2 years of age or in patients with a weight below 10 kg.

The safety of adalimumab in pediatric patients in the polyarticular JIA trials was generally similar to that observed in adults with certain exceptions [see Adverse Reactions (6.1)].

The safety and effectiveness of YUSIMRY have not been established in pediatric patients with JIA less than 2 years of age.

Pediatric Crohn's Disease

The safety and effectiveness of YUSIMRY for the treatment of moderately to severely active Crohn's disease have been established in pediatric patients 6 years of age and older. Use of YUSIMRY for this indication is supported by evidence from adequate and well-controlled studies in adults with additional data from a randomized, double-blind, 52-week clinical study of two dose concentrations of adalimumab in 192 pediatric patients (6 years to 17 years of age) [see Adverse Reactions (6.1), Clinical Pharmacology (12.2, 12.3), Clinical Studies (14.6)]. The adverse reaction profile in patients 6 years to 17 years of age was similar to adults.

The safety and effectiveness of YUSIMRY have not been established in pediatric patients with Crohn's disease less than 6 years of age.

8.5 Geriatric Use

In clinical studies of RA (Studies RA-I, RA-II, RA-III, and RA-IV), a total of 519 subjects 65 years of age and older, including 107 subjects 75 years of age and older, received adalimumab. No overall difference in effectiveness was observed between these subjects and younger adult subjects.

The frequency of serious infection and malignancy among adalimumab-treated subjects 65 years of age and older was higher than for those less than 65 years of age. Consider the benefits and risks of YUSIMRY in patients 65 years of age and older. In patients treated with YUSIMRY, closely monitor for the development of infection or malignancy [see Warnings and Precautions (5.1, 5.2)].

10 OVERDOSAGE

Doses up to 10 mg/kg have been administered to patients in clinical trials without evidence of dose-limiting toxicities. In case of overdosage, it is recommended that the patient be monitored for any signs or symptoms of adverse reactions or effects and appropriate symptomatic treatment instituted immediately.

Consider contacting the Poison Help line (1-800-222-1222) or medical toxicologist for additional overdose management recommendations.

11 DESCRIPTION

Adalimumab-aqvh is a tumor necrosis factor blocker. Adalimumab-aqvh is a recombinant human IgG1 monoclonal antibody with human derived heavy and light chain variable regions and human IgG1:k constant regions. Adalimumab-aqvh is produced by recombinant DNA technology in a mammalian cell (Chinese Hamster Ovary (CHO)) expression system and is purified by a process that includes specific viral inactivation and removal steps. It consists of 1330 amino acids and has a molecular weight of approximately 148 kilodaltons.

YUSIMRY (adalimumab-aqvh) injection is supplied as a sterile, preservative-free solution for subcutaneous administration. The drug product is supplied as either a single-dose, prefilled pen (YUSIMRY Pen), or as a single-dose, 1 mL prefilled glass syringe. The solution of YUSIMRY is a clear to slightly opalescent, colorless to slightly yellow solution, with a pH of about 5.3.

Each 40 mg/0.8 mL prefilled syringe or prefilled pen delivers 0.8 mL (40 mg) of drug product. Each 0.8 mL of YUSIMRY contains adalimumab-aqvh (40 mg), glycine (9.61 mg), L-histidine (0.51 mg), L-histidine hydrochloride monohydrate (4.34 mg), polysorbate 80 (0.80 mg), sodium chloride (2.06 mg) and Water for Injection, USP. Sodium hydroxide is added as necessary to adjust the pH.

12 CLINICAL PHARMACOLOGY

12.1 Mechanism of Action

Adalimumab products bind specifically to TNF-alpha and block its interaction with the p55 and p75 cell surface TNF receptors. Adalimumab products also lyse surface TNF expressing cells in vitro in the presence of complement. Adalimumab products do not bind or inactivate lymphotoxin (TNF-beta). TNF is a naturally occurring cytokine that is involved in normal inflammatory and immune responses.

Elevated concentrations of TNF are found in the synovial fluid of patients with RA, JIA, PsA, and AS and play an important role in both the pathologic inflammation and the joint destruction that are hallmarks of these diseases. Increased concentrations of TNF are also found in psoriasis plaques. In Ps, treatment with YUSIMRY may reduce the epidermal thickness and infiltration of inflammatory cells. The relationship between these pharmacodynamic activities and the mechanism(s) by which adalimumab products exert their clinical effects is unknown.

Adalimumab products also modulate biological responses that are induced or regulated by TNF, including changes in the concentrations of adhesion molecules responsible for leukocyte migration (ELAM-1, VCAM-1, and ICAM-1 with an IC50 of 1-2 X 10^-10M).

12.2 Pharmacodynamics

After treatment with adalimumab, a decrease in concentrations of acute phase reactants of inflammation (C-reactive protein [CRP] and erythrocyte sedimentation rate [ESR]) and serum cytokines (IL-6) was observed compared to baseline in patients with rheumatoid arthritis. A decrease in CRP concentrations was also observed in patients with Crohn's disease, ulcerative colitis and hidradenitis suppurativa. Serum concentrations of matrix metalloproteinases (MMP-1 and MMP-3) that produce tissue remodeling responsible for cartilage destruction were also decreased after adalimumab administration.

12.3 Pharmacokinetics

The pharmacokinetics of adalimumab were linear over the dose range of 0.5 to 10 mg/kg following administration of a single intravenous dose (adalimumab products are not approved for intravenous use). Following 20, 40, and 80 mg every other week and every week subcutaneous administration, adalimumab mean serum trough concentrations at steady state increased approximately proportionally with dose in RA patients. The mean terminal half-life was approximately 2 weeks, ranging from 10 to 20 days across studies. Healthy subjects and patients with RA displayed similar adalimumab pharmacokinetics.

Adalimumab exposure in patients treated with 80 mg every other week is estimated to be comparable with that in patients treated with 40 mg every week.

Absorption

The average absolute bioavailability of adalimumab following a single 40 mg subcutaneous dose was 64%. The mean time to reach the maximum concentration was 5.5 days (131 ± 56 hours) and the maximum serum concentration was 4.7 ± 1.6 mcg/mL in healthy subjects following a single 40 mg subcutaneous administration of adalimumab.

Distribution

The distribution volume (Vss) ranged from 4.7 to 6.0 L following intravenous administration of doses ranging from 0.25 to 10 mg/kg in RA patients.

Elimination

The single dose pharmacokinetics of adalimumab in RA patients were determined in several studies with intravenous doses ranging from 0.25 to 10 mg/kg. The systemic clearance of adalimumab is approximately 12 mL/hr. In long-term studies with dosing more than two years, there was no evidence of changes in clearance over time in RA patients.

Patient Population

Rheumatoid Arthritis and Ankylosing Spondylitis: In patients receiving 40 mg adalimumab every other week, adalimumab mean steady-state trough concentrations were approximately 5 mcg/mL and 8 to 9 mcg/mL, without and with MTX concomitant treatment, respectively. Adalimumab concentrations in the synovial fluid from five rheumatoid arthritis patients ranged from 31 to 96% of those in serum. The pharmacokinetics of adalimumab in patients with AS were similar to those in patients with RA.

Psoriatic Arthritis: In patients receiving 40 mg every other week, adalimumab mean steady-state trough concentrations were 6 to 10 mcg/mL and 8.5 to 12 mcg/mL, without and with MTX concomitant treatment, respectively.

Plaque Psoriasis: Adalimumab mean steady-state trough concentration was approximately 5 to 6 mcg/mL during adalimumab 40 mg every other week treatment.

Adult Uveitis: Adalimumab mean steady concentration was approximately 8 to 10 mcg/mL during adalimumab 40 mg every other week treatment.

Adult Hidradenitis Suppurativa: Adalimumab trough concentrations were approximately 7 to 8 mcg/mL at Week 2 and Week 4, respectively, after receiving 160 mg on Week 0 followed by 80 mg on Week 2. Mean steady-state trough concentrations at Week 12 through Week 36 were approximately 7 to 11 mcg/mL during adalimumab 40 mg every week treatment.

Adult Crohn's Disease: Adalimumab mean trough concentrations were approximately 12 mcg/mL at Week 2 and Week 4 after receiving 160 mg on Week 0 followed by 80 mg on Week 2. Mean steady-state trough concentrations were 7 mcg/mL at Week 24 and Week 56 during adalimumab 40 mg every other week treatment.

Adult Ulcerative Colitis: Adalimumab mean trough concentrations were approximately 12 mcg/mL at Week 2 and Week 4 after receiving 160 mg on Week 0 followed by 80 mg on Week 2. Mean steady-state trough concentrations were approximately 8 mcg/mL and 15 mcg/mL at Week 52 after receiving a dose of adalimumab 40 mg every other week and 40 mg every week, respectively.

Anti-Drug Antibody Effects on Pharmacokinetics

Rheumatoid Arthritis: A trend toward higher apparent clearance of adalimumab in the presence of anti-adalimumab antibodies was identified.

Hidradenitis Suppurativa: In subjects with moderate to severe HS, antibodies to adalimumab were associated with reduced serum adalimumab concentrations. In general, the extent of reduction in serum adalimumab concentrations is greater with increasing titers of antibodies to adalimumab.

Specific Populations

Geriatric Patients: A lower clearance with increasing age was observed in patients with RA aged 40 to >75 years.

Pediatric Patients:

Juvenile Idiopathic Arthritis:

- 4 years to 17 years of age: The adalimumab mean steady-state trough concentrations were 6.8 mcg/mL and 10.9 mcg/mL in patients weighing <30 kg receiving 20 mg adalimumab subcutaneously every other week as monotherapy or with concomitant MTX, respectively. The adalimumab mean steady-state trough concentrations were 6.6 mcg/mL and 8.1 mcg/mL in patients weighing ≥30 kg receiving 40 mg adalimumab subcutaneously every other week as monotherapy or with MTX concomitant treatment, respectively.
- 2 years to <4 years of age or 4 years of age and older weighing <15 kg: The adalimumab mean steady-state trough adalimumab concentrations were 6.0 mcg/mL and 7.9 mcg/mL in patients receiving adalimumab subcutaneously every other week as monotherapy or with MTX concomitant treatment, respectively.

Pediatric Crohn's Disease: Adalimumab mean ± SD concentrations were 15.7±6.5 mcg/mL at Week 4 following 160 mg at Week 0 and 80 mg at Week 2, and 10.5±6.0 mcg/mL at Week 52 following 40 mg every other week dosing in patients weighing ≥ 40 kg. Adalimumab mean ± SD concentrations were 10.6±6.1 mcg/mL at Week 4 following dosing 80 mg at Week 0 and 40 mg at Week 2, and 6.9±3.6 mcg/mL at Week 52 following 20 mg every other week dosing in patients weighing < 40 kg.

Male and Female Patients: No gender-related pharmacokinetic differences were observed after correction for a patient's body weight. Healthy subjects and patients with rheumatoid arthritis displayed similar adalimumab pharmacokinetics.

Patients with Renal or Hepatic Impairment: No pharmacokinetic data are available in patients with hepatic or renal impairment.

Rheumatoid factor or CRP concentrations: Minor increases in apparent clearance were predicted in RA patients receiving doses lower than the recommended dose and in RA patients with high rheumatoid factor or CRP concentrations. These increases are not likely to be clinically important.

Drug Interaction Studies:

Methotrexate: MTX reduced adalimumab apparent clearance after single and multiple dosing by 29% and 44% respectively, in patients with RA [see Drug Interactions (7.1)].

13 NONCLINICAL TOXICOLOGY

13.1 Carcinogenesis, Mutagenesis, Impairment of Fertility

Long-term animal studies of adalimumab products have not been conducted to evaluate the carcinogenic potential or its effect on fertility.

14 CLINICAL STUDIES

14.1 Clinical Studies in Rheumatoid Arthritis

The efficacy and safety of adalimumab were assessed in five randomized, double-blind studies in subjects ≥18 years of age with active rheumatoid arthritis (RA) diagnosed according to American College of Rheumatology (ACR) criteria. Subjects had at least 6 swollen and 9 tender joints. Adalimumab was administered subcutaneously in combination with methotrexate (MTX) (12.5 to 25 mg, Studies RA-I, RA-III and RA-V) or as monotherapy (Studies RA-II and RA-V) or with other disease-modifying anti-rheumatic drugs (DMARDs) (Study RA-IV).

Study RA-I evaluated 271 subjects who had failed therapy with at least one but no more than four DMARDs and had inadequate response to MTX. Doses of 20, 40 or 80 mg of adalimumab or placebo were given every other week for 24 weeks.

Study RA-II evaluated 544 subjects who had failed therapy with at least one DMARD. Doses of placebo, 20 or 40 mg of adalimumab were given as monotherapy every other week or weekly for 26 weeks.

Study RA-III evaluated 619 subjects who had an inadequate response to MTX. Subjects received placebo, 40 mg of adalimumab every other week with placebo injections on alternate weeks, or 20 mg of adalimumab weekly for up to 52 weeks. Study RA-III had an additional primary endpoint at 52 weeks of inhibition of disease progression (as detected by X-ray results). Upon completion of the first 52 weeks, 457 subjects enrolled in an open-label extension phase in which 40 mg of adalimumab was administered every other week for up to 5 years.

Study RA-IV assessed safety in 636 subjects who were either DMARD-naive or were permitted to remain on their pre-existing rheumatologic therapy provided that therapy was stable for a minimum of 28 days. Subjects were randomized to 40 mg of adalimumab or placebo every other week for 24 weeks.

Study RA-V evaluated 799 subjects with moderately to severely active RA of less than 3 years duration who were ≥18 years old and MTX naïve. Subjects were randomized to receive either MTX (optimized to 20 mg/week by Week 8), adalimumab 40 mg every other week or adalimumab /MTX combination therapy for 104 weeks. Subjects were evaluated for signs and symptoms, and for radiographic progression of joint damage. The median disease duration among subjects enrolled in the study was 5 months. The median MTX dose achieved was 20 mg.

Clinical Response

The percent of adalimumab treated subjects achieving ACR 20, 50 and 70 responses in Studies RA-II and III are shown in Table 3.

Table 3. ACR Responses in Studies RA-II and RA-III (Percent of Subjects)
 | Study RA-II Monotherapy (26 weeks) |  |  | Study RA-III Methotrexate Combination (24 and 52 weeks)
Response | Placebo N=110 | Adalimumab 40 mg every other week N=113 | Adalimumab 40 mg weekly N=103 | Placebo/MTX N=200 | Adalimumab/MTX 40 mg every other week N=207
ACR20
Month 6 | 19% | 46%a | 53%a | 30% | 63%a
Month 12 | NA | NA | NA | 24% | 59%a
ACR50
Month 6 | 8% | 22%a | 35%a | 10% | 39%a
Month 12 | NA | NA | NA | 10% | 42%a
ACR70
Month 6 | 2% | 12%a | 18%a | 3% | 21%a
Month 12 | NA | NA | NA | 5% | 23%a

a p<0.01, adalimumab vs. placebo

The results of Study RA-I were similar to Study RA-III; subjects receiving adalimumab 40 mg every other week in Study RA-I also achieved ACR 20, 50 and 70 response rates of 65%, 52% and 24%, respectively, compared to placebo responses of 13%, 7% and 3% respectively, at 6 months (p<0.01).

The results of the components of the ACR response criteria for Studies RA-II and RA-III are shown in Table 4. ACR response rates and improvement in all components of ACR response were maintained to Week 104. Over the 2 years in Study RA-III, 20% of adalimumab subjects receiving 40 mg every other week achieved a major clinical response, defined as maintenance of an ACR 70 response over a 6-month period. ACR responses were maintained in similar proportions of subjects for up to 5 years with continuous adalimumab treatment in the open-label portion of Study RA-III.

Table 4. Components of ACR Response in Studies RA-II and RA-III
 | Study RA-II |  |  |  | Study RA-III
Parameter (median) | Placebo N=110 |  | adalimumaba N=113 |  | Placebo/MTX N=200 |  | adalimumaba/MTX N=207
 | Baseline | Wk 26 | Baseline | Wk 26 | Baseline | Wk 24 | Baseline | Wk 24
Number of tender joints (0-68) | 35 | 26 | 31 | 16* | 26 | 15 | 24 | 8*
Number of swollen joints (0-66) | 19 | 16 | 18 | 10* | 17 | 11 | 18 | 5*
Physician global assessmentb | 7.0 | 6.1 | 6.6 | 3.7* | 6.3 | 3.5 | 6.5 | 2.0*
Patient global assessmentc | 7.5 | 6.3 | 7.5 | 4.5* | 5.4 | 3.9 | 5.2 | 2.0*
Painc | 7.3 | 6.1 | 7.3 | 4.1* | 6.0 | 3.8 | 5.8 | 2.1*
Disability index (HAQ)c | 2.0 | 1.9 | 1.9 | 1.5* | 1.5 | 1.3 | 1.5 | 0.8*
CRP (mg/dL) | 3.9 | 4.3 | 4.6 | 1.8* | 1.0 | 0.9 | 1.0 | 0.4*

a 40 mg adalimumab administered every other week
b Visual analogue scale; 0 = best, 10 = worst
c Disability Index of the Health Assessment Questionnaire; 0 = best, 3 = worst, measures the patient’s ability to perform the following: dress/groom, arise, eat, walk, reach, grip, maintain hygiene, and maintain daily activity
* p<0.001, adalimumab vs. placebo, based on mean change from baseline

The time course of ACR 20 response for Study RA-III is shown in Figure 1.

In Study RA-III, 85% of subjects with ACR 20 responses at Week 24 maintained the response at 52 weeks. The time course of ACR 20 response for Study RA-I and Study RA-II were similar.

Figure 1. Study RA-III ACR 20 Responses over 52 Weeks

In Study RA-IV, 53% of subjects treated with adalimumab 40 mg every other week plus standard of care had an ACR 20 response at Week 24 compared to 35% on placebo plus standard of care (p<0.001). No unique adverse reactions related to the combination of adalimumab and other DMARDs were observed.

In Study RA-V with MTX naïve subjects with recent onset RA, the combination treatment with adalimumab plus MTX led to greater percentages of subjects achieving ACR responses than either MTX monotherapy or adalimumab monotherapy at Week 52 and responses were sustained at Week 104 (see Table 5).

Table 5. ACR Response in Study RA-V (Percent of Subjects)
Response | MTXb N=257 | adalimumabc N=274 | adalimumab/MTX N=268
ACR20
Week 52 | 63% | 54% | 73%
Week 104 | 56% | 49% | 69%
ACR50
Week 52 | 46% | 41% | 62%
Week 104 | 43% | 37% | 59%
ACR70
Week 52 | 27% | 26% | 46%
Week 104 | 28% | 28% | 47%
Major Clinical Responsea | 28% | 25% | 49%

a Major clinical response is defined as achieving an ACR70 response for a continuous six-month period
b p<0.05, adalimumab/MTX vs. MTX for ACR 20, p<0.001, adalimumab/MTX vs. MTX for ACR 50 and 70, and Major Clinical Response
c p<0.001, adalimumab/MTX vs. adalimumab

At Week 52, all individual components of the ACR response criteria for Study RA-V improved in the adalimumab/MTX group and improvements were maintained to Week 104.

Radiographic Response

In Study RA-III, structural joint damage was assessed radiographically and expressed as change in Total Sharp Score (TSS) and its components, the erosion score and Joint Space Narrowing (JSN) score, at month 12 compared to baseline. At baseline, the median TSS was approximately 55 in the placebo and 40 mg every other week groups. The results are shown in Table 6. Adalimumab/MTX treated subjects demonstrated less radiographic progression than subjects receiving MTX alone at 52 weeks.

Table 6. Radiographic Mean Changes Over 12 Months in Study RA-III
 | Placebo/MTX | adalimumab/MTX 40 mg every other week | Placebo/MTX-adalimumab/MTX (95% Confidence Interval*) | P-value**
Total Sharp Score | 2.7 | 0.1 | 2.6 (1.4, 3.8) | <0.001
Erosion Score | 1.6 | 0.0 | 1.6 (0.9, 2.2) | <0.001
JSN Score | 1.0 | 0.1 | 0.9 (0.3, 1.4) | 0.002

* 95% confidence intervals for the differences in change scores between MTX and adalimumab.
** Based on rank analysis

In the open-label extension of Study RA-III, 77% of the original subjects treated with any dose of adalimumab were evaluated radiographically at 2 years. Subjects maintained inhibition of structural damage, as measured by the TSS. Fifty-four percent had no progression of structural damage as defined by a change in the TSS of zero or less. Fifty-five percent (55%) of subjects originally treated with 40 mg adalimumab every other week have been evaluated radiographically at 5 years. Subjects had continued inhibition of structural damage with 50% showing no progression of structural damage defined by a change in the TSS of zero or less.

In Study RA-V, structural joint damage was assessed as in Study RA-III. Greater inhibition of radiographic progression, as assessed by changes in TSS, erosion score and JSN was observed in the adalimumab/MTX combination group as compared to either the MTX or adalimumab monotherapy group at Week 52 as well as at Week 104 (see Table 7).

Table 7. Radiographic Mean Change* in Study RA-V
 |  | MTXa N=257 | adalimumaba, b N=274 | adalimumab/MTX N=268
52 Weeks | Total Sharp score | 5.7 (4.2, 7.3) | 3.0 (1.7, 4.3) | 1.3 (0.5, 2.1)
 | Erosion score | 3.7 (2.7, 4.8) | 1.7 (1.0, 2.4) | 0.8 (0.4, 1.2)
 | JSN score | 2.0 (1.2, 2.8) | 1.3 (0.5, 2.1) | 0.5 (0.0, 1.0)
104 Weeks | Total Sharp score | 10.4 (7.7, 13.2) | 5.5 (3.6, 7.4) | 1.9 (0.9, 2.9)
 | Erosion score | 6.4 (4.6, 8.2) | 3.0 (2.0, 4.0) | 1.0 (0.4, 1.6)
 | JSN score | 4.1 (2.7, 5.4) | 2.6 (1.5, 3.7) | 0.9 (0.3, 1.5)

* mean (95% confidence interval)
a p<0.001, adalimumab/MTX vs. MTX at 52 and 104 weeks and for adalimumab/MTX vs. adalimumab at 104 weeks
b p<0.01, for adalimumab/MTX vs. adalimumab at 52 weeks

Physical Function Response

In studies RA-I through IV, adalimumab showed significantly greater improvement than placebo in the disability index of Health Assessment Questionnaire (HAQ-DI) from baseline to the end of study, and significantly greater improvement than placebo in the health-outcomes as assessed by The Short Form Health Survey (SF 36). Improvement was seen in both the Physical Component Summary (PCS) and the Mental Component Summary (MCS).

In Study RA-III, the mean (95% CI) improvement in HAQ-DI from baseline at Week 52 was 0.60 (0.55, 0.65) for the adalimumab subjects and 0.25 (0.17, 0.33) for placebo/MTX (p<0.001) subjects. Sixty-three percent of adalimumab-treated subjects achieved a 0.5 or greater improvement in HAQ-DI at Week 52 in the double-blind portion of the study. Eighty-two percent of these subjects maintained that improvement through Week 104 and a similar proportion of subjects maintained this response through Week 260 (5 years) of open-label treatment. Mean improvement in the SF-36 was maintained through the end of measurement at Week 156 (3 years).

In Study RA-V, the HAQ-DI and the physical component of the SF-36 showed greater improvement (p<0.001) for the adalimumab/MTX combination therapy group versus either the MTX monotherapy or the adalimumab monotherapy group at Week 52, which was maintained through Week 104.

14.2 Clinical Studies in Juvenile Idiopathic Arthritis

The safety and efficacy of adalimumab was assessed in two studies (Studies JIA-I and JIA-II) in subjects with active polyarticular juvenile idiopathic arthritis (JIA).

Study JIA-I

The safety and efficacy of adalimumab were assessed in a multicenter, randomized, withdrawal, double-blind, parallel-group study in 171 subjects who were 4 to 17 years of age with polyarticular JIA. In the study, the subjects were stratified into two groups: MTX-treated or non-MTX-treated. All subjects had to show signs of active moderate or severe disease despite previous treatment with NSAIDs, analgesics, corticosteroids, or DMARDS. Subjects who received prior treatment with any biologic DMARDS were excluded from the study.

The study included four phases: an open-label lead in phase (OL-LI; 16 weeks), a double-blind randomized withdrawal phase (DB; 32 weeks), an open-label extension phase (OLE-BSA; up to 136 weeks), and an open-label fixed dose phase (OLE-FD; 16 weeks). In the first three phases of the study, adalimumab was administered based on body surface area at a dose of 24 mg/m^2 up to a maximum total body dose of 40 mg subcutaneously (SC) every other week. In the OLE-FD phase, the subjects were treated with 20 mg of adalimumab SC every other week if their weight was less than 30 kg and with 40 mg of adalimumab SC every other week if their weight was 30 kg or greater. Subjects remained on stable doses of NSAIDs and or prednisone (≤0.2 mg/kg/day or 10 mg/day maximum).

Subjects demonstrating a Pediatric ACR 30 response at the end of OL-LI phase were randomized into the double blind (DB) phase of the study and received either adalimumab or placebo every other week for 32 weeks or until disease flare. Disease flare was defined as a worsening of ≥30% from baseline in ≥3 of 6 Pediatric ACR core criteria, ≥2 active joints, and improvement of >30% in no more than 1 of the 6 criteria. After 32 weeks or at the time of disease flare during the DB phase, subjects were treated in the open-label extension phase based on the BSA regimen (OLE-BSA), before converting to a fixed dose regimen based on body weight (OLE-FD phase).

Study JIA-I Clinical Response

At the end of the 16-week OL-LI phase, 94% of the subjects in the MTX stratum and 74% of the subjects in the non-MTX stratum were Pediatric ACR 30 responders. In the DB phase significantly fewer subjects who received adalimumab experienced disease flare compared to placebo, both without MTX (43% vs. 71%) and with MTX (37% vs. 65%). More subjects treated with adalimumab continued to show pediatric ACR 30/50/70 responses at Week 48 compared to subjects treated with placebo. Pediatric ACR responses were maintained for up to two years in the OLE phase in subjects who received adalimumab throughout the study.

Study JIA-II

Adalimumab was assessed in an open-label, multicenter study in 32 subjects who were 2 to <4 years of age or 4 years of age and older weighing <15 kg with moderately to severely active polyarticular JIA. Most subjects (97%) received at least 24 weeks of adalimumab treatment dosed 24 mg/m^2 up to a maximum of 20 mg every other week as a single SC injection up to a maximum of 120 weeks duration. During the study, most subjects used concomitant MTX, with fewer reporting use of corticosteroids or NSAIDs. The primary objective of the study was evaluation of safety [see Adverse Reactions (6.1)]

14.3 Clinical Studies in Psoriatic Arthritis

The safety and efficacy of adalimumab was assessed in two randomized, double-blind, placebo controlled studies in 413 subjects with psoriatic arthritis (PsA). Upon completion of both studies, 383 subjects enrolled in an open-label extension study, in which 40 mg adalimumab was administered every other week.

Study PsA-I enrolled 313 adult subjects with moderately to severely active PsA (>3 swollen and >3 tender joints) who had an inadequate response to NSAID therapy in one of the following forms: (1) distal interphalangeal (DIP) involvement (N=23); (2) polyarticular arthritis (absence of rheumatoid nodules and presence of plaque psoriasis) (N=210); (3) arthritis mutilans (N=1); (4) asymmetric PsA (N=77); or (5) AS-like (N=2). Subjects on MTX therapy (158 of 313 subjects) at enrollment (stable dose of ≤30 mg/week for >1 month) could continue MTX at the same dose. Doses of adalimumab 40 mg or placebo every other week were administered during the 24-week double-blind period of the study.

Compared to placebo, treatment with adalimumab resulted in improvements in the measures of disease activity (see Table 8 and 9). Among subjects with PsA who received adalimumab, the clinical responses were apparent in some subjects at the time of the first visit (two weeks) and were maintained up to 88 weeks in the ongoing open-label study. Similar responses were seen in subjects with each of the subtypes of psoriatic arthritis, although few subjects were enrolled with the arthritis mutilans and ankylosing spondylitis-like subtypes. Responses were similar in subjects who were or were not receiving concomitant MTX therapy at baseline.

Subjects with psoriatic involvement of at least three percent body surface area (BSA) were evaluated for Psoriatic Area and Severity Index (PASI) responses. At 24 weeks, the proportions of subjects achieving a 75% or 90% improvement in the PASI were 59% and 42% respectively, in the adalimumab group (N=69), compared to 1% and 0% respectively, in the placebo group (N=69) (p<0.001). PASI responses were apparent in some subjects at the time of the first visit (two weeks). Responses were similar in subjects who were or were not receiving concomitant MTX therapy at baseline.

Table 8. ACR Response in Study PsA-I (Percent of Subjects)
 | Placebo N=162 | adalimumaba N=151
ACR20
Week 12 | 14% | 58%
Week 24 | 15% | 57%
ACR50
Week 12 | 4% | 36%
Week 24 | 6% | 39%
ACR70
Week 12 | 1% | 20%
Week 24 | 1% | 23%

a p<0.001 for all comparisons between adalimumab and placebo

Table 9. Components of Disease Activity in Study PsA-I
 | Placebo N= 162 |  | adalimumab* N=151
Parameter: median | Baseline | 24 weeks | Baseline | 24 weeks
Number of tender jointsa | 23.0 | 17.0 | 20.0 | 5.0
Number of swollen jointsb | 11.0 | 9.0 | 11.0 | 3.0
Physician global assessmentc | 53.0 | 49.0 | 55.0 | 16.0
Patient global assessmentc | 49.5 | 49.0 | 48.0 | 20.0
Painc | 49.0 | 49.0 | 54.0 | 20.0
Disability index (HAQ)d | 1.0 | 0.9 | 1.0 | 0.4
CRP (mg/dL)e | 0.8 | 0.7 | 0.8 | 0.2

* p<0.001 for adalimumab vs. placebo comparisons based on median changes
a Scale 0-78
b Scale 0-76
c Visual analog scale; 0=best, 100=worst
d Disability Index of the Health Assessment Questionnaire; 0=best, 3=worst; measures the patient’s ability to perform the following: dress/groom, arise, eat, walk, reach, grip, maintain hygiene, and maintain daily activity.
e Normal range: 0-0.287 mg/dL

Similar results were seen in an additional, 12-week study in 100 subjects with moderate to severe psoriatic arthritis who had suboptimal response to DMARD therapy as manifested by ≥3 tender joints and ≥3 swollen joints at enrollment.

Radiographic Response

Radiographic changes were assessed in the PsA studies. Radiographs of hands, wrists, and feet were obtained at baseline and Week 24 during the double-blind period when subjects were on adalimumab or placebo and at Week 48 when all subjects were on open-label adalimumab. A modified Total Sharp Score (mTSS), which included distal interphalangeal joints (i.e., not identical to the TSS used for rheumatoid arthritis), was used by readers blinded to treatment group to assess the radiographs.

Adalimumab-treated subjects demonstrated greater inhibition of radiographic progression compared to placebo-treated subjects and this effect was maintained at 48 weeks (see Table 10).

Table 10. Change in Modified Total Sharp Score in Psoriatic Arthritis
 | Placebo N=141 | adalimumab N=133
 | Week 24 | Week 24 | Week 48
Baseline mean | 22.1 | 23.4 | 23.4
Mean Change ± SD | 0.9 ± 3.1 | -0.1 ± 1.7 | -0.2 ± 4.9 [<0.001 for the difference between adalimumab, Week 48 and Placebo, Week 24 (primary analysis)]

Physical Function Response

In Study PsA-I, physical function and disability were assessed using the HAQ Disability Index (HAQ-DI) and the SF-36 Health Survey. Subjects treated with 40 mg of adalimumab every other week showed greater improvement from baseline in the HAQ-DI score (mean decreases of 47% and 49% at Weeks 12 and 24 respectively) in comparison to placebo (mean decreases of 1% and 3% at Weeks 12 and 24 respectively). At Weeks 12 and 24, subjects treated with adalimumab showed greater improvement from baseline in the SF-36 Physical Component Summary score compared to subjects treated with placebo, and no worsening in the SF-36 Mental Component Summary score. Improvement in physical function based on the HAQ-DI was maintained for up to 84 weeks through the open-label portion of the study.

14.4 Clinical Studies in Ankylosing Spondylitis

The safety and efficacy of adalimumab 40 mg every other week was assessed in 315 adult subjects in a randomized, 24 week double-blind, placebo-controlled study in subjects with active ankylosing spondylitis (AS) who had an inadequate response to glucocorticoids, NSAIDs, analgesics, methotrexate or sulfasalazine. Active AS was defined as subjects who fulfilled at least two of the following three criteria: (1) a Bath AS disease activity index (BASDAI) score ≥4 cm, (2) a visual analog score (VAS) for total back pain ≥ 40 mm, and (3) morning stiffness ≥ 1 hour. The blinded period was followed by an open-label period during which subjects received adalimumab 40 mg every other week subcutaneously for up to an additional 28 weeks.

Improvement in measures of disease activity was first observed at Week 2 and maintained through 24 weeks as shown in Figure 2 and Table 11.

Responses of subjects with total spinal ankylosis (n=11) were similar to those without total ankylosis.

Figure 2. ASAS 20 Response By Visit, Study AS-I

At 12 weeks, the ASAS 20/50/70 responses were achieved by 58%, 38%, and 23%, respectively, of subjects receiving adalimumab, compared to 21%, 10%, and 5% respectively, of subjects receiving placebo (p <0.001). Similar responses were seen at Week 24 and were sustained in subjects receiving open-label adalimumab for up to 52 weeks.

A greater proportion of subjects treated with adalimumab (22%) achieved a low level of disease activity at 24 weeks (defined as a value <20 [on a scale of 0 to 100 mm] in each of the four ASAS response parameters) compared to subjects treated with placebo (6%).

Table 11. Components of Ankylosing Spondylitis Disease Activity
 | Placebo N=107 |  | adalimumab N=208
 | Baseline mean | Week 24 mean | Baseline mean | Week 24 mean
ASAS 20 Response Criteriaa
Patient's Global Assessment of Disease Activitya,b | 65 | 60 | 63 | 38
Total back paina | 67 | 58 | 65 | 37
Inflammationa,c | 6.7 | 5.6 | 6.7 | 3.6
BASFIa,d | 56 | 51 | 52 | 34
BASDAIe scorea | 6.3 | 5.5 | 6.3 | 3.7
BASMIf scorea | 4.2 | 4.1 | 3.8 | 3.3
Tragus to wall (cm) | 15.9 | 15.8 | 15.8 | 15.4
Lumbar flexion (cm) | 4.1 | 4.0 | 4.2 | 4.4
Cervical rotation (degrees) | 42.2 | 42.1 | 48.4 | 51.6
Lumbar side flexion (cm) | 8.9 | 9.0 | 9.7 | 11.7
Intermalleolar distance (cm) | 92.9 | 94.0 | 93.5 | 100.8
CRPa,g | 2.2 | 2.0 | 1.8 | 0.6

a statistically significant for comparisons between adalimumab and placebo at Week 24
b Percent of subjects with at least a 20% and 10-unit improvement measured on a Visual Analog Scale (VAS) with 0 = “none” and 100 = “severe”
c mean of questions 5 and 6 of BASDAI (defined in ‘d’)
d Bath Ankylosing Spondylitis Functional Index
e Bath Ankylosing Spondylitis Disease Activity Index
f Bath Ankylosing Spondylitis Metrology Index
g C-Reactive Protein (mg/dL)

A second randomized, multicenter, double-blind, placebo-controlled study of 82 subjects with ankylosing spondylitis showed similar results.

Subjects treated with adalimumab achieved improvement from baseline in the Ankylosing Spondylitis Quality of Life Questionnaire (ASQoL) score (-3.6 vs. -1.1) and in the Short Form Health Survey (SF-36) Physical Component Summary (PCS) score (7.4 vs. 1.9) compared to placebo-treated subjects at Week 24.

14.5 Clinical Studies in Adults with Crohn’s Disease

The safety and efficacy of multiple doses of adalimumab were assessed in adult subjects with moderately to severely active Crohn’s disease, CD, (Crohn’s Disease Activity Index (CDAI) ≥ 220 and ≤ 450) in randomized, double-blind, placebo-controlled studies. Concomitant stable doses of aminosalicylates, corticosteroids, and/or immunomodulatory agents were permitted, and 79% of subjects continued to receive at least one of these medications.

Induction of clinical remission (defined as CDAI < 150) was evaluated in two studies. In Study CD-I, 299 TNF-blocker naïve subjects were randomized to one of four treatment groups: the placebo group received placebo at Weeks 0 and 2, the 160/80 group received 160 mg adalimumab at Week 0 and 80 mg at Week 2, the 80/40 group received 80 mg at Week 0 and 40 mg at Week 2, and the 40/20 group received 40 mg at Week 0 and 20 mg at Week 2. Clinical results were assessed at Week 4.

In the second induction study, Study CD-II, 325 subjects who had lost response to, or were intolerant to, previous infliximab therapy were randomized to receive either 160 mg adalimumab at Week 0 and 80 mg at Week 2, or placebo at Weeks 0 and 2. Clinical results were assessed at Week 4.

Maintenance of clinical remission was evaluated in Study CD-III. In this study, 854 subjects with active disease received open-label adalimumab, 80 mg at Week 0 and 40 mg at Week 2. Subjects were then randomized at Week 4 to 40 mg adalimumab every other week, 40 mg adalimumab every week, or placebo. The total study duration was 56 weeks. Subjects in clinical response (decrease in CDAI ≥70) at Week 4 were stratified and analyzed separately from those not in clinical response at Week 4.

Induction of Clinical Remission

A greater percentage of the subjects treated with 160/80 mg adalimumab achieved induction of clinical remission versus placebo at Week 4 regardless of whether the subjects were TNF blocker naïve (CD-I), or had lost response to or were intolerant to infliximab (CD-II) (see Table 12).

Table 12. Induction of Clinical Remission in Studies CD-I and CD-II (Percent of Subjects)
 | CD-I |  | CD-II
 | Placebo N=74 | adalimumab 160/80 mg N=76 | Placebo N=166 | adalimumab 160/80 mg N=159
Week 4
Clinical remission | 12% | 36%a | 7% | 21%a
Clinical response | 34% | 58%b | 34% | 52%b

Clinical remission is CDAI score < 150; clinical response is decrease in CDAI of at least 70 points.
a p<0.001 for adalimumab vs. placebo pairwise comparison of proportions
b p<0.01 for adalimumab vs. placebo pairwise comparison of proportions

Maintenance of Clinical Remission

In Study CD-III at Week 4, 58% (499/854) of subjects were in clinical response and were assessed in the primary analysis. At Weeks 26 and 56, greater proportions of subjects who were in clinical response at Week 4 achieved clinical remission in the adalimumab 40 mg every other week maintenance group compared to subjects in the placebo maintenance group (see Table 13). The group that received adalimumab therapy every week did not demonstrate significantly higher remission rates compared to the group that received adalimumab every other week.

Table 13. Maintenance of Clinical Remission in CD-III (Percent of Subjects)
 | Placebo N=170 | 40 mg adalimumab every other week N=172
Week 26
Clinical remission | 17% | 40%a
Clinical response | 28% | 54%a
Week 56
Clinical remission | 12% | 36%a
Clinical response | 18% | 43%a

Clinical remission is CDAI score < 150; clinical response is decrease in CDAI of at least 70 points.
a p<0.001 for adalimumab vs. placebo pairwise comparisons of proportions

Of those in response at Week 4 who attained remission during the study, subjects in the adalimumab every other week group maintained remission for a longer time than subjects in the placebo maintenance group. Among subjects who were not in response by Week 12, therapy continued beyond 12 weeks did not result in significantly more responses.

14.6 Clinical Studies in Pediatric Subjects with Crohn’s Disease

A randomized, double-blind, 52-week clinical study of 2 dose concentrations of adalimumab (Study PCD-I) was conducted in 192 pediatric subjects (6 to 17 years of age) with moderately to severely active Crohn’s disease (defined as Pediatric Crohn’s Disease Activity Index (PCDAI) score > 30). Enrolled subjects had over the previous two-year period an inadequate response to corticosteroids or an immunomodulator (i.e., azathioprine, 6-mercaptopurine, or methotrexate). Subjects who had previously received a TNF blocker were allowed to enroll if they had previously had loss of response or intolerance to that TNF blocker.

Subjects received open-label induction therapy at a dose based on their body weight (≥40 kg and <40 kg). Subjects weighing ≥40 kg received 160 mg (at Week 0) and 80 mg (at Week 2). Subjects weighing <40 kg received 80 mg (at Week 0) and 40 mg (at Week 2). At Week 4, subjects within each body weight category (≥40 kg and <40 kg) were randomized 1:1 to one of two maintenance dose regimens (high dose and low dose). The high dose was 40 mg every other week for subjects weighing ≥40 kg and 20 mg every other week for subjects weighing <40 kg. The low dose was 20 mg every other week for subjects weighing ≥40 kg and 10 mg every other week for subjects weighing <40 kg.

Concomitant stable dosages of corticosteroids (prednisone dosage ≤40 mg/day or equivalent) and immunomodulators (azathioprine, 6-mercaptopurine, or methotrexate) were permitted throughout the study.

At Week 12, subjects who experienced a disease flare (increase in PCDAI of ≥ 15 from Week 4 and absolute PCDAI > 30) or who were non-responders (did not achieve a decrease in the PCDAI of ≥ 15 from baseline for 2 consecutive visits at least 2 weeks apart) were allowed to dose-escalate (i.e., switch from blinded every other week dosing to blinded every week dosing); subjects who dose-escalated were considered treatment failures.

At baseline, 38% of subjects were receiving corticosteroids, and 62% of subjects were receiving an immunomodulator. Forty-four percent (44%) of subjects had previously lost response or were intolerant to a TNF blocker. The median baseline PCDAI score was 40.
Of the 192 subjects total, 188 subjects completed the 4 week induction period, 152 subjects completed 26 weeks of treatment, and 124 subjects completed 52 weeks of treatment. Fifty-one percent (51%) (48/95) of subjects in the low maintenance dose group dose-escalated, and 38% (35/93) of subjects in the high maintenance dose group dose-escalated.
At Week 4, 28% (52/188) of subjects were in clinical remission (defined as PCDAI ≤ 10).

The proportions of subjects in clinical remission (defined as PCDAI ≤ 10) and clinical response (defined as reduction in PCDAI of at least 15 points from baseline) were assessed at Weeks 26 and 52.

At both Weeks 26 and 52, the proportion of subjects in clinical remission and clinical response was numerically higher in the high dose group compared to the low dose group (Table 14). The recommended maintenance regimen is 20 mg every other week for subjects weighing < 40 kg and 40 mg every other week for subjects weighing ≥ 40 kg. Every week dosing is not the recommended maintenance dosing regimen [see Dosage and Administration (2.3)].

Table 14. Clinical Remission and Clinical Response in Study PCD-1
 | Low Maintenance Dose† (20 or 10 mg every other week) N = 95 | High Maintenance Dose# (40 or 20 mg every other week) N = 93
Week 26
Clinical Remission‡ | 28% | 39%
Clinical Response§ | 48% | 59%
Week 52
Clinical Remission‡ | 23% | 33%
Clinical Response§ | 28% | 42%

† The low maintenance dose was 20 mg every other week for subjects weighing ≥ 40 kg and 10 mg every other week for subjects weighing < 40 kg.
# The high maintenance dose was 40 mg every other week for subjects weighing ≥ 40 kg and 20 mg every other week for subjects weighing < 40 kg.
‡ Clinical remission defined as PCDAI ≤ 10.
§ Clinical response defined as reduction in PCDAI of at least 15 points from baseline.

14.7 Clinical Studies in Adults with Ulcerative Colitis

The safety and efficacy of adalimumab were assessed in adult subjects with moderately to severely active ulcerative colitis (Mayo score 6 to 12 on a 12 point scale, with an endoscopy subscore of 2 to 3 on a scale of 0 to 3) despite concurrent or prior treatment with immunosuppressants such as corticosteroids, azathioprine, or 6-MP in two randomized, double-blind, placebo-controlled clinical studies (Studies UC-I and UC-II). Both studies enrolled TNF-blocker naïve subjects, but Study UC-II also allowed entry of subjects who lost response to or were intolerant to TNF-blockers. Forty percent (40%) of subjects enrolled in Study UC-II had previously used another TNF-blocker.

Concomitant stable doses of aminosalicylates and immunosuppressants were permitted. In Studies UC-I and II, subjects were receiving aminosalicylates (69%), corticosteroids (59%) and/or azathioprine or 6-MP (37%) at baseline. In both studies, 92% of subjects received at least one of these medications.

Induction of clinical remission (defined as Mayo score ≤ 2 with no individual subscores > 1) at Week 8 was evaluated in both studies. Clinical remission at Week 52 and sustained clinical remission (defined as clinical remission at both Weeks 8 and 52) were evaluated in Study UC-II.

In Study UC-I, 390 TNF-blocker naïve subjects were randomized to one of three treatment groups for the primary efficacy analysis. The placebo group received placebo at Weeks 0, 2, 4 and 6. The 160/80 group received 160 mg adalimumab at Week 0 and 80 mg at Week 2, and the 80/40 group received 80 mg adalimumab at Week 0 and 40 mg at Week 2. After Week 2, subjects in both adalimumab treatment groups received 40 mg every other week.

In Study UC-II, 518 subjects were randomized to receive either adalimumab 160 mg at Week 0, 80 mg at Week 2, and 40 mg every other week starting at Week 4 through Week 50, or placebo starting at Week 0 and every other week through Week 50. Corticosteroid taper was permitted starting at Week 8.

In both Studies UC-I and UC-II, a greater percentage of the subjects treated with 160/80 mg of adalimumab compared to subjects treated with placebo achieved induction of clinical remission. In Study UC-II, a greater percentage of the subjects treated with 160/80 mg of adalimumab compared to subjects treated with placebo achieved sustained clinical remission (clinical remission at both Weeks 8 and 52) (Table 15).

Table 15. Induction of Clinical Remission in Studies UC-I and UC-II and Sustained Clinical Remission in Study UC-II (Percent of Subjects)
 | Study UC-I |  |  | Study UC-II
 | Placebo N=130 | adalimumab 160/80 mg N=130 | Treatment Difference (95% CI) | Placebo N=246 | adalimumab 160/80 mg N=248 | Treatment Difference (95% CI)
Induction of Clinical Remission (Clinical Remission at Week 8) | 9.2% | 18.5% | 9.3%a (0.9%, 17.6%) | 9.3% | 16.5% | 7.2%a (1.2%, 12.9%)
Sustained Clinical Remission (Clinical Remission at both Weeks 8 and 52) | N/A | N/A | N/A | 4.1% | 8.5% | 4.4%a (0.1%, 8.6%)

Clinical remission is defined as Mayo score ≤ 2 with no individual subscores > 1.
CI=Confidence interval
a p<0.05 for adalimumab vs. placebo pairwise comparison of proportions

In Study UC-I, there was no statistically significant difference in clinical remission observed between the adalimumab 80/40 mg group and the placebo group at Week 8.

In Study UC-II, 17.3% (43/248) in the adalimumab group were in clinical remission at Week 52 compared to 8.5% (21/246) in the placebo group (treatment difference: 8.8%; 95% confidence interval (CI): [2.8%, 14.5%]; p<0.05).

In the subgroup of subjects in Study UC-II with prior TNF-blocker use, the treatment difference for induction of clinical remission appeared to be lower than that seen in the whole study population, and the treatment differences for sustained clinical remission and clinical remission at Week 52 appeared to be similar to those seen in the whole study population. The subgroup of subjects with prior TNF-blocker use achieved induction of clinical remission at 9% (9/98) in the adalimumab group versus 7% (7/101) in the placebo group, and sustained clinical remission at 5% (5/98) in the adalimumab group versus 1% (1/101) in the placebo group. In the subgroup of subjects with prior TNF-blocker use, 10% (10/98) were in clinical remission at Week 52 in the adalimumab group versus 3% (3/101) in the placebo group.

14.8 Clinical Studies in Plaque Psoriasis

The safety and efficacy of adalimumab were assessed in randomized, double-blind, placebo-controlled studies in 1696 adult subjects with moderate to severe chronic plaque psoriasis (Ps) who were candidates for systemic therapy or phototherapy.

Study Ps-I evaluated 1212 subjects with chronic Ps with ≥10% body surface area (BSA) involvement, Physician's Global Assessment (PGA) of at least moderate disease severity, and Psoriasis Area and Severity Index (PASI) ≥12 within three treatment periods. In period A, subjects received placebo or adalimumab at an initial dose of 80 mg at Week 0 followed by a dose of 40 mg every other week starting at Week 1. After 16 weeks of therapy, subjects who achieved at least a PASI 75 response at Week 16, defined as a PASI score improvement of at least 75% relative to baseline, entered period B and received open-label 40 mg adalimumab every other week. After 17 weeks of open label therapy, subjects who maintained at least a PASI 75 response at Week 33 and were originally randomized to active therapy in period A were re-randomized in period C to receive 40 mg adalimumab every other week or placebo for an additional 19 weeks. Across all treatment groups the mean baseline PASI score was 19 and the baseline Physician's Global Assessment score ranged from “moderate” (53%) to "severe" (41%) to "very severe" (6%).

Study Ps-II evaluated 99 subjects randomized to adalimumab and 48 subjects randomized to placebo with chronic plaque psoriasis with ≥10% BSA involvement and PASI ≥12. Subjects received placebo, or an initial dose of 80 mg adalimumab at Week 0 followed by 40 mg every other week starting at Week 1 for 16 weeks. Across all treatment groups the mean baseline PASI score was 21 and the baseline PGA score ranged from “moderate” (41%) to "severe" (51%) to "very severe" (8%).

Studies Ps-I and II evaluated the proportion of subjects who achieved "clear" or "minimal" disease on the 6-point PGA scale and the proportion of subjects who achieved a reduction in PASI score of at least 75% (PASI 75) from baseline at Week 16 (see Table 16 and Table 17).

Additionally, Study Ps-I evaluated the proportion of subjects who maintained a PGA of “clear” or “minimal” disease or a PASI 75 response after Week 33 and on or before Week 52.

Table 16. Efficacy Results at 16 Weeks in Study Ps-I Number of Subjects (%)
 | adalimumab 40 mg every other week N = 814 | Placebo N = 398
PGA: Clear or minimal a | 506 (62%) | 17 (4%)
PASI 75 | 578 (71%) | 26 (7%)

a Clear = no plaque elevation, no scale, plus or minus hyperpigmentation or diffuse pink or red coloration, Minimal = possible but difficult to ascertain whether there is slight elevation of plaque above normal skin, plus or minus surface dryness with some white coloration, plus or minus up to red coloration

Table 17. Efficacy Results at 16 Weeks in Study Ps-II Number of Subjects (%)
 | adalimumab 40 mg every other week N = 99 | Placebo N = 48
PGA: Clear or minimala | 70 (71%) | 5 (10%)
PASI 75 | 77 (78%) | 9 (19%)

a Clear = no plaque elevation, no scale, plus or minus hyperpigmentation or diffuse pink or red coloration, Minimal = possible but difficult to ascertain whether there is slight elevation of plaque above normal skin, plus or minus surface dryness with some white coloration, plus or minus up to red coloration

Additionally, in Study Ps-I, subjects on adalimumab who maintained a PASI 75 were re-randomized to adalimumab (N = 250) or placebo (N = 240) at Week 33. After 52 weeks of treatment with adalimumab, more subjects on adalimumab maintained efficacy when compared to subjects who were re-randomized to placebo based on maintenance of PGA of "clear" or "minimal" disease (68% vs. 28%) or a PASI 75 (79% vs. 43%).

A total of 347 stable responders participated in a withdrawal and retreatment evaluation in an open-label extension study. Median time to relapse (decline to PGA "moderate" or worse) was approximately 5 months. During the withdrawal period, no subject experienced transformation to either pustular or erythrodermic psoriasis. A total of 178 subjects who relapsed re-initiated treatment with 80 mg of adalimumab, then 40 mg every other week beginning at Week 1. At Week 16, 69% (123/178) of subjects had a response of PGA "clear" or "minimal".

A randomized, double-blind study (Study Ps-III) compared the efficacy and safety of adalimumab versus placebo in 217 adult subjects. Subjects in the study had to have chronic plaque psoriasis of at least moderate severity on the PGA scale, fingernail involvement of at least moderate severity on a 5-point Physician's Global Assessment of Fingernail Psoriasis (PGA-F) scale, a Modified Nail Psoriasis Severity Index (mNAPSI) score for the target-fingernail of ≥ 8, and either a BSA involvement of at least 10% or a BSA involvement of at least 5% with a total mNAPSI score for all fingernails of ≥ 20. Subjects received an initial dose of 80 mg adalimumab followed by 40 mg every other week (starting one week after the initial dose) or placebo for 26 weeks followed by open-label adalimumab treatment for an additional 26 weeks. This study evaluated the proportion of subjects who achieved "clear" or "minimal" assessment with at least a 2-grade improvement on the PGA-F scale and the proportion of subjects who achieved at least a 75% improvement from baseline in the mNAPSI score (mNAPSI 75) at Week 26.

At Week 26, a higher proportion of subjects in the adalimumab group than in the placebo group achieved the PGA-F endpoint. Furthermore, a higher proportion of subjects in the adalimumab group than in the placebo group achieved mNAPSI 75 at Week 26 (see Table 18).

Table 18. Efficacy Results at 26 Weeks
Endpoint | adalimumab 40 mg every other week [Subjects received 80 mg of adalimumab at Week 0, followed by 40 mg every other week starting at Week 1.] N=109 | Placebo N=108
PGA-F: ≥2-grade improvement and clear or minimal | 49% | 7%
mNAPSI 75 | 47% | 3%

Nail pain was also evaluated and improvement in nail pain was observed in Study Ps-III.

14.9 Clinical Studies in Hidradenitis Suppurativa

Two randomized, double-blind, placebo-controlled studies (Studies HS-I and II) evaluated the safety and efficacy of adalimumab in a total of 633 adult subjects with moderate to severe hidradenitis suppurativa (HS) with Hurley Stage II or III disease and with at least 3 abscesses or inflammatory nodules. In both studies, subjects received placebo or adalimumab at an initial dose of 160 mg at Week 0, 80 mg at Week 2, and 40 mg every week starting at Week 4 and continued through Week 11. Subjects used topical antiseptic wash daily. Concomitant oral antibiotic use was allowed in Study HS-II.

Both studies evaluated Hidradenitis Suppurativa Clinical Response (HiSCR) at Week 12. HiSCR was defined as at least a 50% reduction in total abscess and inflammatory nodule count with no increase in abscess count and no increase in draining fistula count relative to baseline (see Table 19). Reduction in HS-related skin pain was assessed using a Numeric Rating Scale in subjects who entered the study with an initial baseline score of 3 or greater on a 11-point scale. In both studies, a higher proportion of adalimumab- than placebo-treated subjects achieved HiSCR (see Table 19).

Table 19. Efficacy Results at 12 Weeks in Subjects with Moderate to Severe Hidradenitis Suppurativa
 | HS Study I |  | HS Study II [19.3% of subjects in Study HS-II continued baseline oral antibiotic therapy during the study.]
 | Placebo | adalimumab 40 mg Weekly | Placebo | adalimumab 40 mg Weekly
Hidradenitis Suppurativa Clinical Response (HiSCR) | N = 154 40 (26%) | N = 153 64 (42%) | N=163 45 (28%) | N=163 96 (59%)

In both studies, from Week 12 to Week 35 (Period B), subjects who had received adalimumab were re-randomized to 1 of 3 treatment groups (adalimumab 40 mg every week, adalimumab 40 mg every other week, or placebo). Subjects who had been randomized to placebo were assigned to receive adalimumab 40 mg every week (Study HS-I) or placebo (Study HS-II).

During Period B, flare of HS, defined as ≥25% increase from baseline in abscesses and inflammatory nodule counts and with a minimum of 2 additional lesions, was documented in 22 (22%) of the 100 subjects who were withdrawn from adalimumab treatment following the primary efficacy timepoint in two studies.

14.10 Clinical Studies in Adults with Uveitis

The safety and efficacy of adalimumab were assessed in adult subjects with non-infectious intermediate, posterior and panuveitis excluding subjects with isolated anterior uveitis, in two randomized, double-masked, placebo-controlled studies (UV I and II). Subjects received placebo or adalimumab at an initial dose of 80 mg followed by 40 mg every other week starting one week after the initial dose. The primary efficacy endpoint in both studies was ´time to treatment failure´.

Treatment failure was a multi-component outcome defined as the development of new inflammatory chorioretinal and/or inflammatory retinal vascular lesions, an increase in anterior chamber (AC) cell grade or vitreous haze (VH) grade or a decrease in best corrected visual acuity (BCVA).

Study UV I evaluated 217 subjects with active uveitis while being treated with corticosteroids (oral prednisone at a dose of 10 to 60 mg/day). All subjects received a standardized dose of prednisone 60 mg/day at study entry followed by a mandatory taper schedule, with complete corticosteroid discontinuation by Week 15.

Study UV II evaluated 226 subjects with inactive uveitis while being treated with corticosteroids (oral prednisone 10 to 35 mg/day) at baseline to control their disease. Subjects subsequently underwent a mandatory taper schedule, with complete corticosteroid discontinuation by Week 19.

Clinical Response

Results from both studies demonstrated statistically significant reduction of the risk of treatment failure in subjects treated with adalimumab versus subjects receiving placebo. In both studies, all components of the primary endpoint contributed cumulatively to the overall difference between adalimumab and placebo groups (Table 20).

Table 20. Time to Treatment Failure in Studies UV I and UV II
 | UV I |  |  | UV II
 | Placebo (N = 107) | adalimumab (N = 110) | HR [95% CI]a | Placebo (N = 111) | adalimumab (N = 115) | HR [95% CI]a
Failureb n (%) | 84 (78.5) | 60 (54.5) | 0.50 [0.36, 0.70] | 61 (55.0) | 45 (39.1) | 0.57 [0.39, 0.84]
Median Time to Failure (Months) [95% CI] | 3.0 [2.7, 3.7] | 5.6 [3.9, 9.2] | N/A | 8.3 [4.8, 12.0] | NEc | N/A

ª HR of adalimumab versus placebo from proportional hazards regression with treatment as factor.
b Treatment failure at or after Week 6 in Study UV I, or at or after Week 2 in Study UV II, was counted as event. Subjects who discontinued the study were censored at the time of dropping out.
c NE = not estimable. Fewer than half of at-risk subjects had an event.

Figure 3. Kaplan-Meier Curves Summarizing Time to Treatment Failure on or after Week 6 (Study UV I) or Week 2 (Study UV II)

Study UV I

Study UV II

Note: P# = Placebo (Number of Events/Number at Risk); A# = adalimumab (Number of Events/Number at Risk).

15 REFERENCES

1. National Cancer Institute. Surveillance, Epidemiology, and End Results Database (SEER) Program. SEER Incidence Crude Rates, 17 Registries, 2000-2007.

16 HOW SUPPLIED/STORAGE AND HANDLING

YUSIMRY (adalimumab-aqvh) is supplied as a preservative-free, sterile, clear to slightly opalescent, colorless to slightly yellow solution for subcutaneous administration. The following packaging configurations are available:

- YUSIMRY Pen Carton - 40 mg/0.8 mL

YUSIMRY is supplied in a carton containing two dose trays. Each dose tray consists of a single-dose pen, containing a 1 mL prefilled glass syringe with a fixed ½ inch needle, providing 40 mg/0.8 mL of YUSIMRY. The needle cover is not manufactured from natural rubber latex. The NDC number is 71288-815-81.

- Prefilled Syringe Carton - 40 mg/0.8 mL

YUSIMRY is supplied in a carton containing two dose trays. Each dose tray consists of a single-dose, 1 mL prefilled glass syringe with a fixed ½ inch needle, providing 40 mg/0.8 mL of YUSIMRY. The needle cover is not manufactured from natural rubber latex. The NDC number is 71288-816-81.

Storage and Stability

Do not use beyond the expiration date on the container. YUSIMRY must be refrigerated at 36°F to 46°F (2°C to 8°C). DO NOT FREEZE. Do not use if frozen, even if it has been thawed.

Store in original carton until time of administration to protect from light.

If needed, for example when traveling, YUSIMRY may be stored at room temperature up to a maximum of 77°F (25°C) for a period of up to 14 days, with protection from light. YUSIMRY should be discarded if not used within the 14-day period. Record the date when YUSIMRY is first removed from the refrigerator in the spaces provided on the carton and dose pack.

Do not store YUSIMRY in extreme heat or cold.

17 PATIENT COUNSELING INFORMATION

Advise the patient or caregiver to read the FDA-approved patient labeling (Medication Guide and Instructions for Use).

Infections

Inform patients that YUSIMRY may lower the ability of their immune system to fight infections. Instruct patients of the importance of contacting their doctor if they develop any symptoms of infection, including tuberculosis, invasive fungal infections, and reactivation of hepatitis B virus infections [see Warnings and Precautions (5.1, 5.2, 5.4)].

Malignancies

Counsel patients about the risk of malignancies while receiving YUSIMRY [see Warnings and Precautions (5.2)].

Hypersensitivity Reactions

Advise patients to seek immediate medical attention if they experience any symptoms of severe hypersensitivity reactions [see Warnings and Precautions (5.3)].

Other Medical Conditions

Advise patients to report any signs of new or worsening medical conditions such as congestive heart failure, neurological disease, autoimmune disorders, or cytopenias. Advise patients to report any symptoms suggestive of a cytopenia such as bruising, bleeding, or persistent fever [see Warnings and Precautions (5.5, 5.6, 5.8, 5.9)].

Instructions on Injection Technique

Inform patients that the first injection is to be performed under the supervision of a qualified health care professional. If a patient or caregiver is to administer YUSIMRY, instruct them in injection techniques and assess their ability to inject subcutaneously to ensure the proper administration of YUSIMRY [see Instructions for Use].

For patients who will use the YUSIMRY Pen, tell them that they:

- Will hear two "clicks" during the YUSIMRY injection. The first 'click' means the start of injection and second 'click' means the end of injection.
- To start injection, push the pen body down. Continue holding down after hearing the first 'click'.
- In the viewing window, the orange indicator will advance to show the progress of the injection.
- When injection has finished, there will be a second 'click' and the 'Orange Indicator' will completely block the viewing window.

Instruct patients to dispose of their used needles and syringes in a FDA-cleared sharps disposal container immediately after use. Instruct patients not to dispose of loose needles and syringes or pens in their household trash. Instruct patients that if they do not have a FDA-cleared sharps disposal container, they may use a household container that is made of a heavy-duty plastic, can be closed with a tight-fitting and puncture-resistant lid without sharps being able to come out, upright and stable during use, leak-resistant, and properly labeled to warn of hazardous waste inside the container.

Instruct patients that when their sharps disposal container is almost full, they will need to follow their community guidelines for the correct way to dispose of their sharps disposal container. Instruct patients that there may be state or local laws regarding disposal of used needles and syringes. Refer patients to the FDA's website at http://www.fda.gov/safesharpsdisposal for more information about safe sharps disposal, and for specific information about sharps disposal in the state that they live in.

Instruct patients not to dispose of their used sharps disposal container in their household trash unless their community guidelines permit this. Instruct patients not to recycle their used sharps disposal container.

Manufactured for: Meitheal Pharmaceuticals

Chicago, IL 60631 (USA)
©2025 Meitheal Pharmaceuticals Inc.

Manufactured by: Hong Kong King-Friend Industrial Company Limited, Hong Kong, China 999077
US License No. 2375

YUSIMRY is a trademark of Hong Kong King-Friend.

Revised: November 2025

PCR-750-20746

MEDICATION GUIDE
YUSIMRY® (Ue sim ree)
(adalimumab-aqvh)
injection, for subcutaneous use

Read the Medication Guide that comes with YUSIMRY before you start taking it and each time you get a refill. There may be new information. This Medication Guide does not take the place of talking with your healthcare provider about your medical condition or treatment.

What is the most important information I should know about YUSIMRY?
YUSIMRY is a medicine that affects your immune system. YUSIMRY can lower the ability of your immune system to fight infections. Serious infections have happened in people taking adalimumab products. These serious infections include tuberculosis (TB) and infections caused by viruses, fungi or bacteria that have spread throughout the body. Some people have died from these infections.

- Your healthcare provider should test you for TB before starting YUSIMRY.
- Your healthcare provider should check you closely for signs and symptoms of TB during treatment with YUSIMRY.

You should not start taking YUSIMRY if you have any kind of infection unless your healthcare provider says it is okay.

Before starting YUSIMRY, tell your healthcare provider if you:

- think you have an infection or have symptoms of an infection such as:
  - fever, sweats, or chills
  - muscle aches
  - cough
  - shortness of breath
  - blood in phlegm
  - warm, red, or painful skin or sores on your body
  - diarrhea or stomach pain
  - burning when you urinate or urinate more often than normal
  - feel very tired
  - weight loss
- are being treated for an infection.
- get a lot of infections or have infections that keep coming back.
- have diabetes.
- have TB, or have been in close contact with someone with TB.
- were born in, lived in, or traveled to countries where there is more risk for getting TB. Ask your healthcare provider if you are not sure.
- live or have lived in certain parts of the country (such as the Ohio and Mississippi River valleys) where there is an increased risk for getting certain kinds of fungal infections (histoplasmosis, coccidioidomycosis, or blastomycosis). These infections may happen or become more severe if you use YUSIMRY. Ask your healthcare provider if you do not know if you have lived in an area where these infections are common.
- have or have had hepatitis B.
- use the medicine ORENCIA (abatacept), KINERET (anakinra), RITUXAN (rituximab), IMURAN (azathioprine), or PURINETHOL (6–mercaptopurine, 6-MP).
- are scheduled to have major surgery.

After starting YUSIMRY, call your healthcare provider right away if you have an infection, or any sign of an infection.
YUSIMRY can make you more likely to get infections or make any infection that you may have worse.

Cancer

- For children and adults taking Tumor Necrosis Factor (TNF)-blockers, including YUSIMRY, the chances of getting cancer may increase.
- There have been cases of unusual cancers in children, teenagers, and young adults using TNF-blockers.
- People with rheumatoid arthritis (RA), especially more serious RA, may have a higher chance for getting a kind of cancer called lymphoma.
- If you use TNF blockers, including YUSIMRY, your chance of getting two types of skin cancer may increase (basal cell cancer and squamous cell cancer of the skin). These types of cancer are generally not life-threatening if treated. Tell your healthcare provider if you have a bump or open sore that does not heal.
- Some people receiving TNF blockers including YUSIMRY developed a rare type of cancer called hepatosplenic T-cell lymphoma. This type of cancer often results in death. Most of these people were male teenagers or young men. Also, most people were being treated for Crohn's disease or ulcerative colitis with another medicine called IMURAN (azathioprine) or PURINETHOL (6–mercaptopurine, 6–MP).

What is YUSIMRY?
YUSIMRY is a medicine called a Tumor Necrosis Factor (TNF)-blocker. YUSIMRY is used:

- To reduce the signs and symptoms of:
  - moderate to severe RA in adults. YUSIMRY can be used alone, with methotrexate, or with certain other medicines.
  - moderate to severe polyarticular juvenile idiopathic arthritis (JIA) in children 2 years and older. YUSIMRY can be used alone or with methotrexate.
  - psoriatic arthritis (PsA) in adults. YUSIMRY can be used alone or with certain other medicines.
  - ankylosing spondylitis (AS) in adults.
  - moderate to severe hidradenitis suppurativa (HS) in adults.
- To treat moderate to severe Crohn's disease (CD) in adults and children 6 years of age and older.
- To treat moderate to severe ulcerative colitis (UC) in adults. It is not known if adalimumab products are effective in people who stopped responding to or could not tolerate TNF-blocker medicines.
- To treat moderate to severe chronic (lasting a long time) plaque psoriasis (Ps) in adults who have the condition in many areas of their body and who may benefit from taking injections or pills (systemic therapy) or phototherapy (treatment using ultraviolet light alone or with pills).
- To treat non-infectious intermediate, posterior, and panuveitis in adults

What should I tell my healthcare provider before taking YUSIMRY?
YUSIMRY may not be right for you. Before starting YUSIMRY, tell your healthcare provider about all of your medical conditions, including if you:

- have an infection. See "What is the most important information I should know about YUSIMRY?"
- have or have had cancer.
- have any numbness or tingling or have a disease that affects your nervous system such as multiple sclerosis or Guillain-Barré syndrome.
- have or had heart failure.
- have recently received or are scheduled to receive a vaccine. You may receive vaccines, except for live vaccines while using YUSIMRY. Children should be brought up to date with all vaccines before starting YUSIMRY.
- are allergic to YUSIMRY or to any of its ingredients. See the end of this Medication Guide for a list of ingredients in YUSIMRY.
- are pregnant or plan to become pregnant, breastfeeding or plan to breastfeed. You and your healthcare provider should decide if you should take YUSIMRY while you are pregnant or breastfeeding.
- have a baby and you were using YUSIMRY during your pregnancy. Tell your baby's healthcare provider before your baby receives any vaccines.

Tell your healthcare provider about all the medicines you take, including prescription and over-the-counter medicines, vitamins, and herbal supplements.
Especially tell your healthcare provider if you use:

- ORENCIA (abatacept), KINERET (anakinra), REMICADE (infliximab), ENBREL (etanercept), CIMZIA (certolizumab pegol) or SIMPONI (golimumab), because you should not use YUSIMRY while you are also using one of these medicines.
- RITUXAN (rituximab). Your healthcare provider may not want to give you YUSIMRY if you have received RITUXAN (rituximab) recently.
- IMURAN (azathioprine) or PURINETHOL (6–mercaptopurine, 6-MP).

Keep a list of your medicines with you to show your healthcare provider and pharmacist each time you get a new medicine.

How should I take YUSIMRY?

- YUSIMRY is given by an injection under the skin. Your healthcare provider will tell you how often to take an injection of YUSIMRY. This is based on your condition to be treated. Do not inject YUSIMRY more often than you were prescribed.
- See the Instructions for Use inside the carton for complete instructions for the right way to prepare and inject YUSIMRY.
- Make sure you have been shown how to inject YUSIMRY before you do it yourself. You can call your healthcare provider or 1-888-808-5529 if you have any questions about giving yourself an injection. Someone you know can also help you with your injection after they have been shown how to prepare and inject YUSIMRY.
- Do not try to inject YUSIMRY yourself until you have been shown the right way to give the injections. If your healthcare provider decides that you or a caregiver may be able to give your injections of YUSIMRY at home, you should receive training on the right way to prepare and inject YUSIMRY.
- Do not miss any doses of YUSIMRY unless your healthcare provider says it is okay. If you forget to take YUSIMRY, inject a dose as soon as you remember. Then, take your next dose at your regular scheduled time. This will put you back on schedule. In case you are not sure when to inject YUSIMRY, call your healthcare provider or pharmacist.
- If you take more YUSIMRY than you were told to take, call your healthcare provider.

What are the possible side effects of YUSIMRY?
YUSIMRY can cause serious side effects, including:
See "What is the most important information I should know about YUSIMRY?"

- Serious Infections.
  Your healthcare provider will examine you for TB and perform a test to see if you have TB. If your healthcare provider feels that you are at risk for TB, you may be treated with medicine for TB before you begin treatment with YUSIMRY and during treatment with YUSIMRY. Even if your TB test is negative your healthcare provider should carefully monitor you for TB infections while you are taking YUSIMRY. People who had a negative TB skin test before receiving adalimumab products have developed active TB. Tell your healthcare provider if you have any of the following symptoms while taking or after taking YUSIMRY:
  - cough that does not go away
  - low grade fever
  - weight loss
  - loss of body fat and muscle (wasting)
- Hepatitis B infection in people who carry the virus in their blood.
  If you are a carrier of the hepatitis B virus (a virus that affects the liver), the virus can become active while you use YUSIMRY. Your healthcare provider should do blood tests before you start treatment, while you are using YUSIMRY, and for several months after you stop treatment with YUSIMRY.
  Tell your healthcare provider if you have any of the following symptoms of a possible hepatitis B infection:
  - muscle aches
  - feel very tired
  - dark urine
  - skin or eyes look yellow
  - little or no appetite
  - vomiting
  - clay-colored bowel movements
  - fever
  - chills
  - stomach discomfort
  - skin rash
- Allergic reactions. Allergic reactions can happen in people who use YUSIMRY. Call your healthcare provider or get medical help right away if you have any of these symptoms of a serious allergic reaction:
  - hives
  - trouble breathing
  - swelling of your face, eyes, lips, or mouth
- Nervous system problems. Signs and symptoms of a nervous system problem include: numbness or tingling, problems with your vision, weakness in your arms or legs, and dizziness.
- Blood problems. Your body may not make enough of the blood cells that help fight infections or help to stop bleeding. Symptoms include a fever that does not go away, bruising or bleeding very easily, or looking very pale.
- New heart failure or worsening of heart failure you already have. Call your healthcare provider right away if you get new worsening symptoms of heart failure while taking YUSIMRY, including:
  - shortness of breath
  - sudden weight gain
  - swelling of your ankles or feet
- Immune reactions including a lupus-like syndrome. Symptoms include chest discomfort or pain that does not go away, shortness of breath, joint pain, or a rash on your cheeks or arms that gets worse in the sun. Symptoms may improve when you stop YUSIMRY.
- Liver problems. Liver problems can happen in people who use TNF-blocker medicines.
  These problems can lead to liver failure and death. Call your healthcare provider right away if you have any of these symptoms:
  - feel very tired
  - poor appetite or vomiting
  - skin or eyes look yellow
  - pain on the right side of your stomach (abdomen)
- Psoriasis. Some people using adalimumab products had new psoriasis or worsening of psoriasis they already had. Tell your healthcare provider if you develop red scaly patches or raised bumps that are filled with pus. Your healthcare provider may decide to stop your treatment with YUSIMRY.

Call your healthcare provider or get medical care right away if you develop any of the above symptoms. Your treatment with YUSIMRY may be stopped.

The most common side effects of YUSIMRY include:

- injection site reactions: redness, rash, swelling, itching, or bruising. These symptoms usually will go away within a few days. Call your healthcare provider right away if you have pain, redness or swelling around the injection site that does not go away within a few days or gets worse.
- upper respiratory infections (including sinus infections).
- headaches.
- rash.

These are not all the possible side effects with YUSIMRY. Tell your healthcare provider if you have any side effect that bothers you or that does not go away. Ask your healthcare provider or pharmacist for more information.
Call your doctor for medical advice about side effects. You may report side effects to FDA at 1-800-FDA-1088.

How should I store YUSIMRY?

- Store YUSIMRY in the refrigerator at 36°F to 46°F (2°C to 8°C). Store YUSIMRY in the original carton until use to protect it from light.
- Do not freeze YUSIMRY. Do not use YUSIMRY if frozen, even if it has been thawed.
- Refrigerated YUSIMRY may be used until the expiration date printed on the YUSIMRY carton, dose tray, Pen or prefilled syringe. Do not use YUSIMRY after the expiration date.
- If needed, for example when you are traveling, you may also store YUSIMRY at room temperature up to 77°F (25°C) for up to 14 days. Store YUSIMRY in the original carton until use to protect it from light.
- Throw away YUSIMRY if it has been kept at room temperature and not been used within 14 days.
- Record the date you first remove YUSIMRY from the refrigerator in the spaces provided on the carton and dose tray.
- Do not store YUSIMRY in extreme heat or cold.
- Do not use a Pen or prefilled syringe if the liquid is cloudy, discolored, or has flakes or particles in it.
- Do not drop or crush YUSIMRY. The prefilled syringe is glass.

Keep YUSIMRY, injection supplies, and all other medicines out of the reach of children.

General information about the safe and effective use of YUSIMRY.
Medicines are sometimes prescribed for purposes other than those listed in a Medication Guide. Do not use YUSIMRY for a condition for which it was not prescribed. Do not give YUSIMRY to other people, even if they have the same condition. It may harm them.
This Medication Guide summarizes the most important information about YUSIMRY. If you would like more information, talk with your healthcare provider. You can ask your pharmacist or healthcare provider for information about YUSIMRY that is written for health professionals.

What are the ingredients in YUSIMRY?
Active ingredient: adalimumab-aqvh

YUSIMRY Pen 40 mg/0.8 mL and YUSIMRY prefilled syringe 40 mg/0.8 mL:

Inactive ingredients: glycine, L-histidine, L-histidine hydrochloride monohydrate, polysorbate 80, sodium chloride, and Water for Injection. Sodium hydroxide is added as necessary to adjust the pH.

Manufactured for: Meitheal Pharmaceuticals

Chicago, IL 60631 (USA)
©2024 Meitheal Pharmaceuticals Inc.

Manufactured by: Hong Kong King-Friend Industrial Company Limited, Hong Kong, China 999077

US License No. 2375
For more information, go to www.YUSIMRY.com or call Meitheal Pharmaceuticals at -1-888-808-5529.

This Medication Guide has been approved by the U.S. Food and Drug Administration.

Revised: 10/2024

PCR-750-19767

INSTRUCTIONS FOR USE
YUSIMRY® (Ue sim' ree)
(adalimumab-aqvh)
40 mg/ 0.8 mL
SINGLE-DOSE PREFILLED SYRINGE

Do not try to inject YUSIMRY yourself until you have been shown the right way to give the injections and have read and understand this Instructions for Use. If your healthcare provider decides that you or a caregiver may be able to give your injections of YUSIMRY at home, you should receive training on the right way to prepare and inject YUSIMRY. It is important that you read, understand, and follow these instructions so that you inject YUSIMRY the right way.

It is also important to talk to your healthcare provider to be sure you understand your YUSIMRY dosing instructions. To help you remember when to inject YUSIMRY, you can mark your calendar ahead of time. Call your healthcare provider if you or your caregiver have any questions about the right way to inject YUSIMRY.

YUSIMRY Single-Dose Prefilled Syringe

Important Information You Need to Know Before Injecting YUSIMRY

Do not use the prefilled syringe and call your healthcare provider or pharmacist if:

- Liquid is cloudy, discolored, or has flakes or particles in it
- Expiration date has passed
- Liquid has been frozen (even if thawed) or left in direct sunlight
- The prefilled syringe has been dropped or crushed.

Keep the needle cover on until right before your injection.

How should I store YUSIMRY?

- Store YUSIMRY in the refrigerator between 36°F to 46°F (2°C to 8°C).
- Store YUSIMRY in the original carton until use to protect it from light.
- Do not freeze.
- Refrigerated YUSIMRY may be used until the expiration date printed on the YUSIMRY carton, dose tray or prefilled syringe.
- If needed, for example when you are traveling, you may also store YUSIMRY at room temperature up to 77°F (25°C) for up to 14 days.
- Throw away YUSIMRY if it has been kept at room temperature and not used within 14 days.
- Record the date you first remove YUSIMRY from the refrigerator in the spaces provided on the carton and dose tray.
- Do not store YUSIMRY in extreme heat or cold.

Keep YUSIMRY, injection supplies, and all other medicines out of reach of children.

Read Instructions on All Pages Before Using the YUSIMRY Single-Dose Prefilled Syringe

Take YUSIMRY out of the refrigerator.

- Leave YUSIMRY at room temperature for 15 to 30 minutes before injecting.
- Do not remove the needle cover while allowing YUSIMRY to reach room temperature.
- Do not warm YUSIMRY in any other way. For example, do not warm it in a microwave or in hot water.
- Do not use the prefilled syringe if liquid has been frozen (even if thawed).

Check expiration date on the prefilled syringe label. Do not use the prefilled syringe if expiration date has passed.
Place the following on a clean, flat surface:

- 1 single-dose prefilled syringe
- 1 alcohol swab (not included)
- 1 cotton ball or gauze pad (not included)
- Puncture-resistant sharps disposal container (not included). See Step 8 at the end of this Instructions for Use for instructions on how to throw away (dispose of) your prefilled syringe.

Wash and dry your hands.

Choose an injection site:

- On the front of your thighs or,
- Your abdomen (belly) at least 2 inches from your navel (belly button).
- Different from your last injection site.

Wipe the injection site in a circular motion with the alcohol swab.

- Do not inject through clothes.
- Do not inject into skin that is sore, bruised, red, hard, scarred, has stretch marks, or areas with psoriasis plaques.

Hold the prefilled syringe in one hand.
Gently pull the needle cover straight off with the other hand.

- Throw the needle cover away.
- Do not touch the needle with your fingers or let the needle touch anything.
- You do not need to remove the air bubble from the syringe.

Hold the body of the prefilled syringe in one hand between the thumb and index fingers. Hold the prefilled syringe in your hand like a pencil.
Do not pull back on the plunger at any time.
Gently squeeze the area of cleaned skin at your injection site with your other hand. Hold the skin firmly.

Insert the needle into the skin at about a 45-degree angle using a quick, dart-like motion.

- After the needle is in, let go of the skin.

Slowly push the plunger all the way in until all of the liquid is injected and the prefilled syringe is empty.

When the injection is completed, slowly pull the needle out of the skin while keeping the prefilled syringe at the same angle.
After completing the injection, place a cotton ball or gauze pad on the skin of the injection site.

- Do not rub.
- Slight bleeding at the injection site is normal.

How should I dispose of the used YUSIMRY prefilled syringe?

- Put your used syringes in a FDA-cleared sharps disposal container right away after use. Do not throw away (dispose of) syringes in the household trash.
- If you do not have a FDA-cleared sharps disposal container, you may use a household container that is:
-
  - made of a heavy-duty plastic,
  - can be closed with a tight-fitting, puncture-resistant lid, without sharps being able to come out,
  - upright and stable during use,
  - leak-resistant, and
  - properly labeled to warn of hazardous waste inside the container.

- When your sharps disposal container is almost full, you will need to follow your community guidelines for the right way to dispose of your sharps disposal container. There may be state or local laws about how you should throw away used syringes. For more information about safe sharps disposal, and for specific information about sharps disposal in the state that you live in, go to the FDA's website at:
  http://www.fda.gov/safesharpsdisposal.
- Do not dispose of your used sharps disposal container in your household trash unless your community guidelines permit this. Do not recycle your used sharps disposal container.

The needle cover, alcohol swab, cotton ball or gauze pad, dose tray, and packaging may be placed in your household trash.

Questions About Using the YUSIMRY Prefilled Syringe
What if I have not received in-person training from a healthcare provider?

- Call your healthcare provider or 1-888-808-5529 or visit www.YUSIMRY.com if you need help.

Always keep the prefilled syringe and the sharps disposal container out of the reach of children.

- Keep a record of the dates and locations of your injections.
- To help you remember when to take YUSIMRY, mark your calendar ahead of time.

meitheal®

Manufactured for Meitheal Pharmaceuticals Chicago, IL 60631 (USA)
Manufactured by Hong Kong King-Friend Industrial Company Limited, Hong Kong, China 999077
US License Number: 2375

This Instructions for Use has been approved by the U.S. Food and Drug Administration. Issued: 10/2024

INSTRUCTIONS FOR USE

YUSIMRY® PEN (ue sim' ree)
(adalimumab-aqvh)
injection, for subcutaneous use
40 mg/ 0.8 mL Single-Dose Prefilled Pen

This Instructions for Use contains information on how to use the YUSIMRY Pen.

Before Injecting: Your healthcare provider should show you how to use the YUSIMRY Pen before you use it for the first time. Call your healthcare provider, 1-888-808-5529 or visit www.YUSIMRY.com if you need help.

YUSIMRY Single-Dose Prefilled Pen

Do not use the prefilled pen and call your healthcare provider or pharmacist if the:

- liquid is cloudy, discolored, or has flakes or particles in it
- expiration date has passed
- liquid has been frozen (even if thawed) or left in direct sunlight
- prefilled pen has been dropped, crushed or damaged in any way

Your dose may require more than 1 injection. For questions, ask your healthcare provider.
Keep the clear cap on the prefilled pen until right before your injection.
Keep the YUSIMRY prefilled pen and all medicines out of the reach of children.

Questions About Using the YUSIMRY Single-Dose Prefilled Pen

What if I have not received in-person training from a healthcare provider?

- Call your healthcare provider if you need help.

Record Your Injections

- Keep a record of the date and locations of your injection sites.
- To help you remember when to take YUSIMRY, mark your calendar ahead of time.

Read All Instructions before Using the YUSIMRY Single-Dose Prefilled Pen.

Take YUSIMRY out of the refrigerator.

- Leave YUSIMRY at room temperature for 15 to 30 minutes before injecting.
- Do not remove the clear cap while allowing YUSIMRY to reach room temperature.
- Do not warm YUSIMRY in any other way. For example, do not warm it in a microwave or in hot water.
- Do not use the prefilled pen if the liquid has been frozen (even if thawed).

Check the expiration date on the prefilled pen label. Do not use the prefilled pen if the expiration date has passed.
Check the viewing window.

- Hold the prefilled pen with the clear cap facing down.
- It is normal to see 1 or more air bubbles in the viewing window.
- Make sure the liquid is clear and colorless.
- Do not use if the prefilled pen has been dropped, crushed or damaged in any way.

Place the following on a clean, flat surface:

- 1 single-dose prefilled pen
- 1 alcohol swab (not included)
- 1 cotton ball or gauze pad (not included)
- Puncture-resistant sharps disposal container (not included). See step 10 for instructions on how to throw away (dispose of) your prefilled pen.

Wash and dry your hands.

Choose an injection site:

- Choose the front of your thighs or your stomach (belly) at least 2 inches from your belly button (navel).
- Change (rotate) your injection site with each injection.
- Do not inject through clothes.
- Do not inject into skin that is sore, bruised, red, hard, scarred, has stretch marks, or areas with psoriasis plaques.

Wipe the injection site in a circular motion with the alcohol swab.

Pull the clear cap straight off.

- It is normal to see a few drops of liquid at the end of the needle.
- Throw away the clear cap.
- Do not replace the clear cap after it has been removed.
- Do not touch the gray needle guard.

Hold the body of the prefilled pen in 1 hand so you can see the viewing window.
Do not press the gray needle guard with your fingers. This could activate the prefilled pen too soon and cause a needlestick injury.
Place the gray needle guard straight against your skin at a 90-degree angle.

Press the prefilled pen firmly against the skin and you will hear the first "Click".
The orange indicator will start to move along the viewing window.

Hold the pen firmly until the orange indicator stops moving and you hear the second "Click".
After you hear the second "Click" hold the pen in place and count to 5.

When the injection is complete, make sure the orange indicator has filled the viewing window before slowly pulling the pen away.
The gray needle guard will cover the needle tip. If there are more than a few drops of liquid on the injection site, call your healthcare provider.
After completing the injection, place a cotton ball or gauze pad on the skin of the injection site.

- Do not rub the injection site.
- Slight bleeding at the injection site is normal.

How should I dispose of the used YUSIMRY prefilled pen

- Put your used pens in a FDA-cleared sharps disposal container right away after use. Do not throw away (dispose of) pens in the household trash.
- If you do not have a FDA-cleared sharps disposal container, you may use a household container that is:
  - made of a heavy-duty plastic,
  - can be closed with a tight-fitting, puncture-resistant lid, without sharps being able to come out
  - upright and stable during use,
  - leak-resistant, and
  - properly labeled to warn of hazardous waste inside the container.
- When your sharps disposal container is almost full, you will need to follow your community guidelines for the right way to dispose of your sharps disposal container. There may be state or local laws about how you should throw away used pens. For more information about safe sharps disposal, and for specific information about sharps disposal in the state that you live in, go to the FDA's website at: http://www.fda.gov/safesharpsdisposal.
- Do not dispose of your used sharps disposal container in your household trash unless your community guidelines permit this. Do not recycle your used sharps disposal container.

Important: Always keep the sharps disposal container out of the reach of children.
The clear cap, alcohol swab, cotton ball or gauze pad, and packaging may be placed in your household trash.

This Instructions for Use has been approved by the U.S. Food and Drug Administration.

Manufactured for Meitheal Pharmaceuticals Chicago, IL 60631 (USA)

©2024 Meitheal Pharmaceuticals Inc.

Manufactured by Hong Kong King-Friend Industrial Company Limited, Hong Kong, China 999077

US License Number: 2375
Approved: 10/2024

PCR-750-19766

PACKAGE LABEL

Carton Label - Two 40 mg/0.8 mL Single-Dose Prefilled Syringes - YUSIMRY

PRINCIPAL DISPLAY PANEL

NDC 71288-816-81

YUSIMRY®
adalimumab-aqvh
Injection

40 mg/0.8 mL Single-Dose Prefilled Syringes

For subcutaneous use only

This carton contains:

- 2 Single-Dose
  Prefilled Syringes
- 1 Medication Guide
- 1 Prescribing Information
- 1 Instructions for Use

Store in refrigerator at 36°F to 46°F
(2°C to 8°C) in orignal carton to
protect from light. DO NOT FREEZE.
Do not use if frozen, even if it has
been thawed. Do not shake.
YUSIMRY® may be stored at room
temperature up to a maximum of
77°F (25°C) for up to 14 days, with
protection from light. Once stored
at room temperature, do not place
back in the refrigerator.

ATTENTION PHARMACIST: Each patient is
required to receive the enclosed Medication Guide.

The entire carton is to be dispensed as a unit.

meitheal®

40 mg/
0.8 mL
2 Single-Dose
Prefilled
Syringes

Rx only

PACKAGE LABEL

Carton Label - Two 40 mg/0.8 mL Single-Dose Pens - YUSIMRY

PRINCIPAL DISPLAY PANEL

NDC 71288-815-81

YUSIMRY® PEN
adalimumab-aqvh
Injection

40 mg/0.8 mL Single-Dose Prefilled Pens

For subcutaneous use only

This carton contains:

- 2 Single-Dose
  Prefilled Pens
- 1 Medication Guide
- 1 Prescribing Information
- 1 Instructions for Use

ATTENTION PHARMACIST:
Each patient is required to receive the enclosed Medication Guide.
The entire carton is to be dispensed as a unit.

Your dose may require more than 1 injection.
For questions, check with your healthcare provider.

Store in refrigerator at 36° to 46°F (2° to 8°C) in
orignal carton to protect from light. DO NOT FREEZE.
Do not use if frozen, even if it has been thawed.
YUSIMRY may be stored at room temperature up to a
maximum of 77°F (25°C) for up to 14 days, with protection
from light. Once stored at room temperature, do not place
back in the refrigerator.

meitheal®

40 mg/
0.8 mL
2 Single-Dose
Prefilled Pens

Rx only